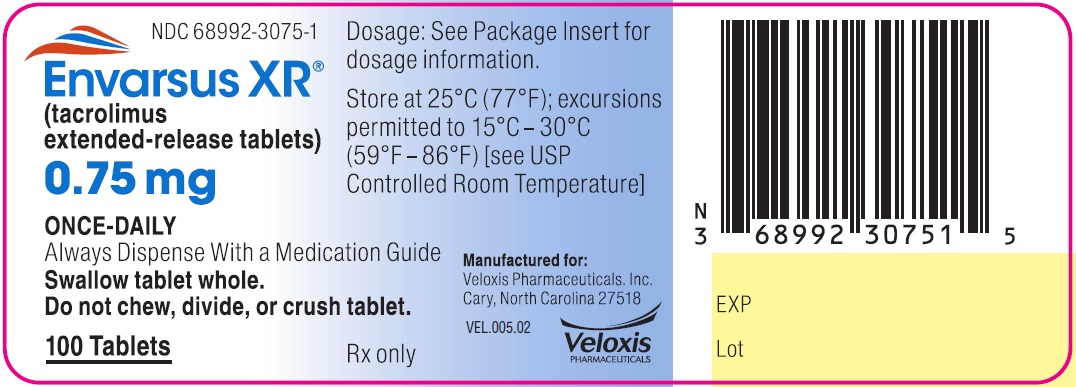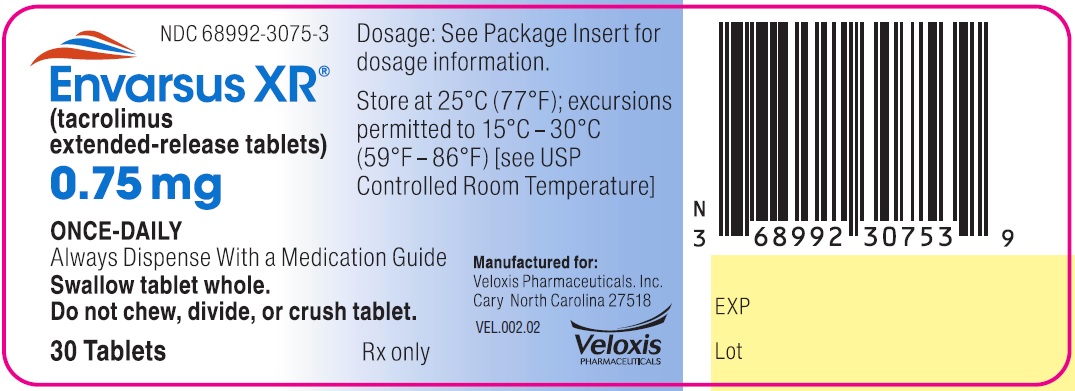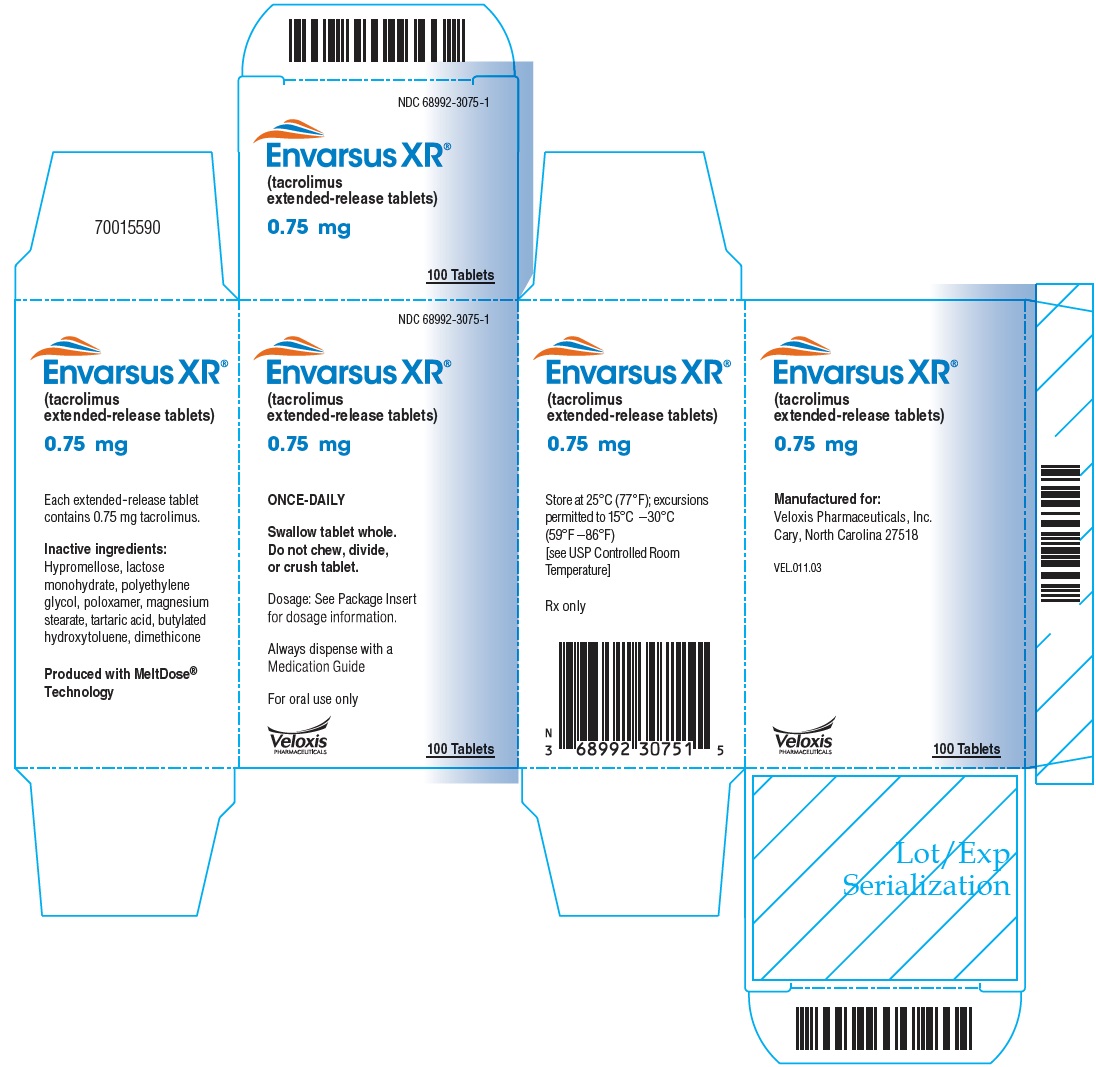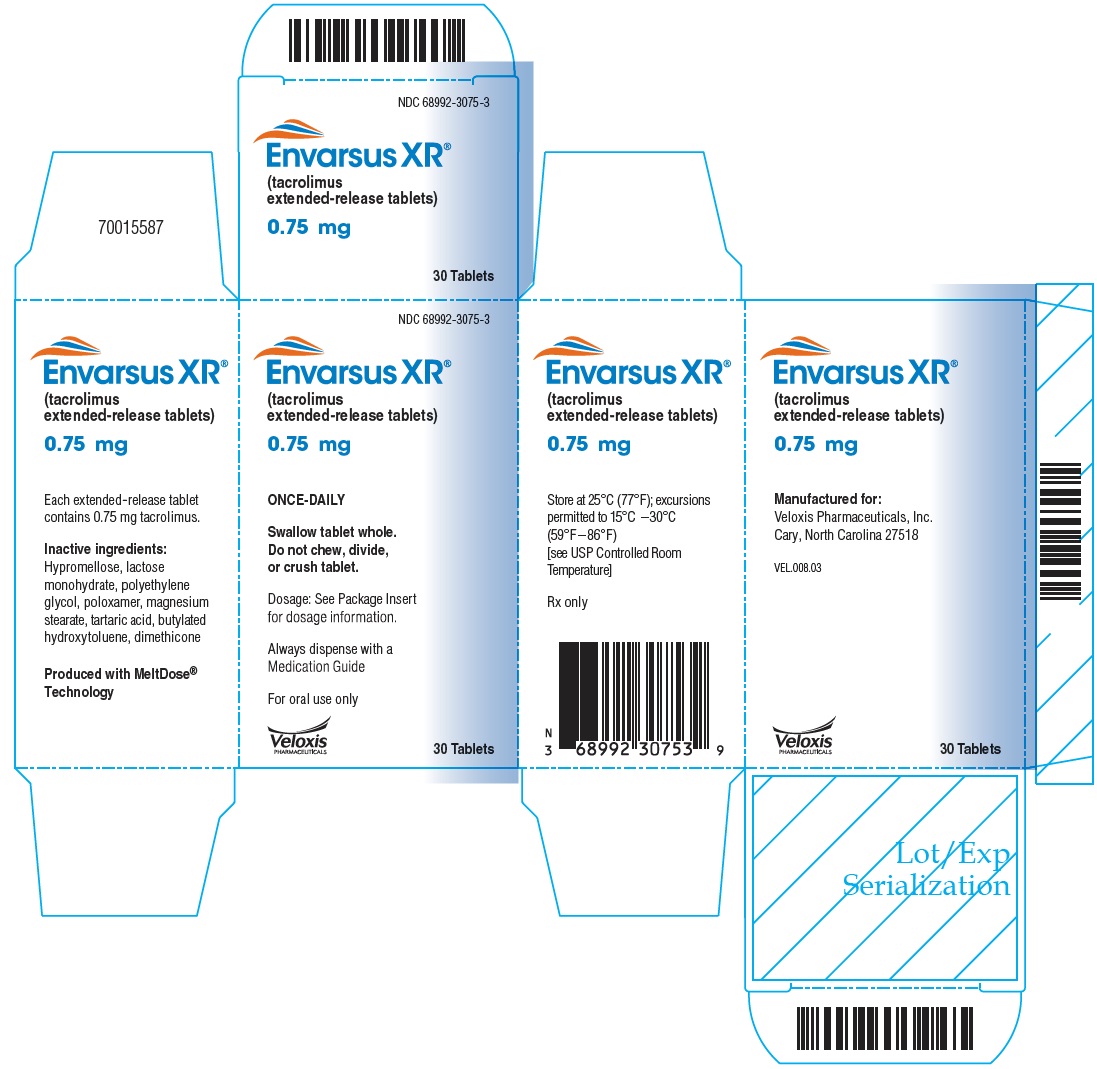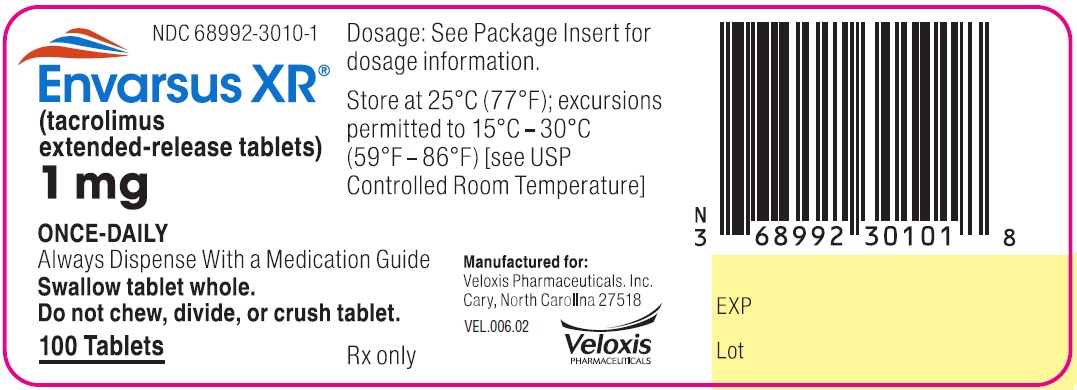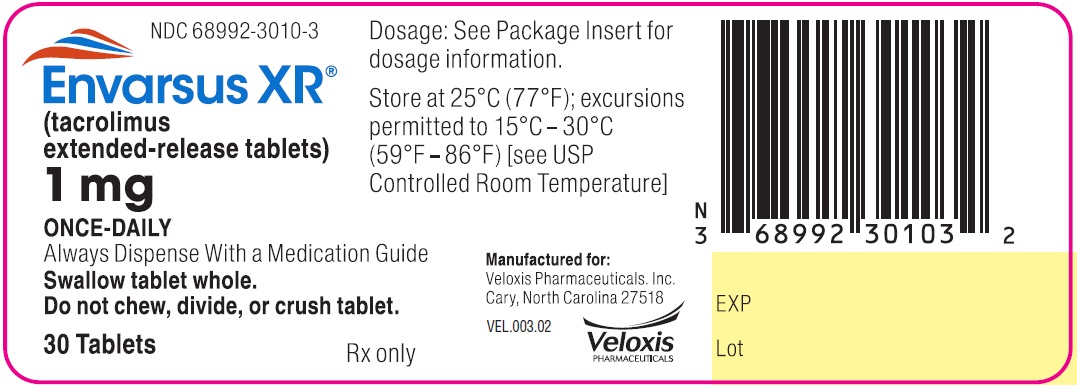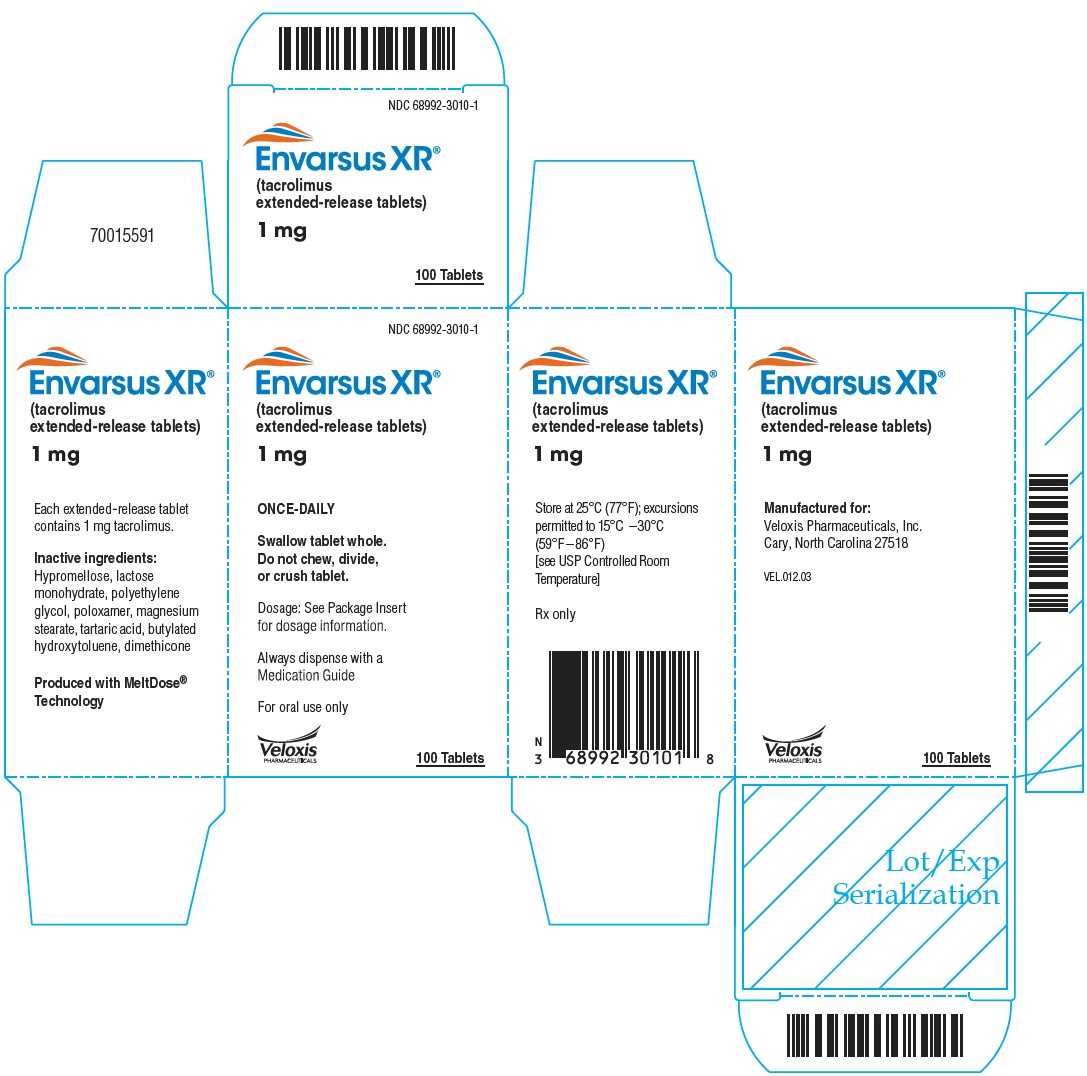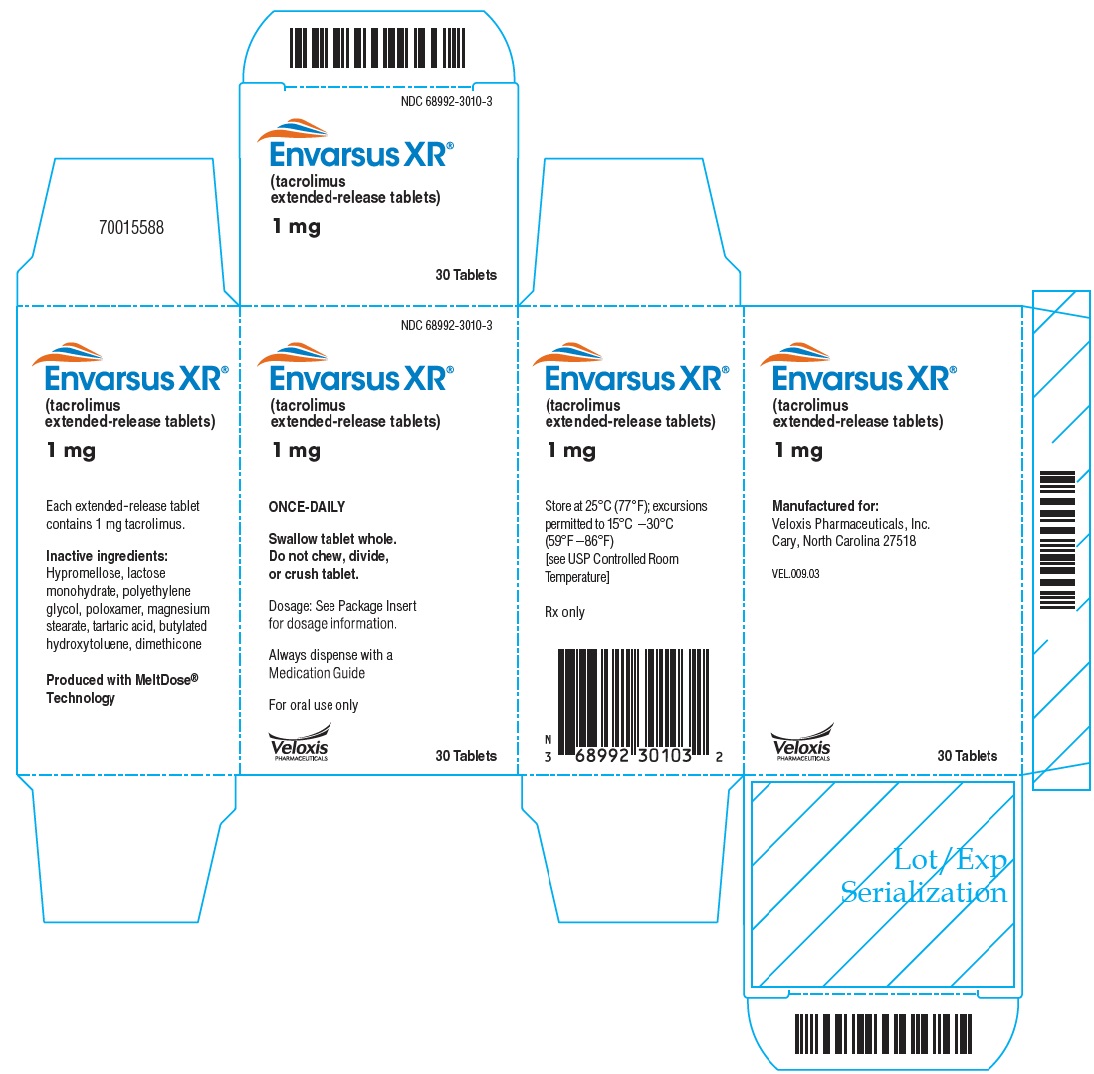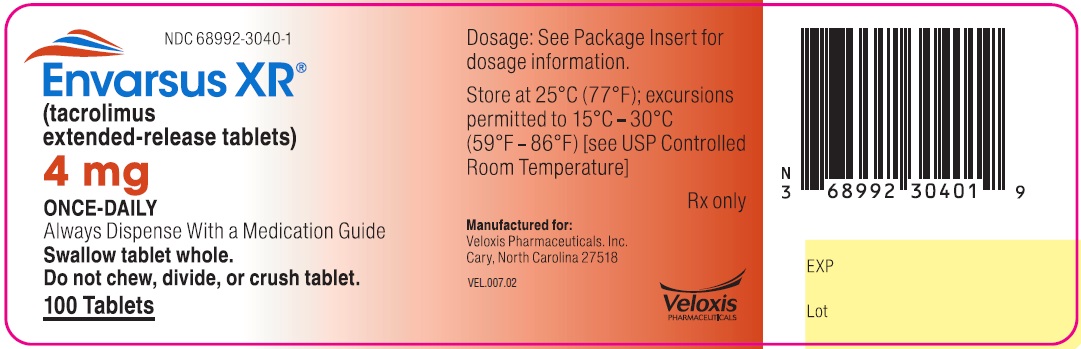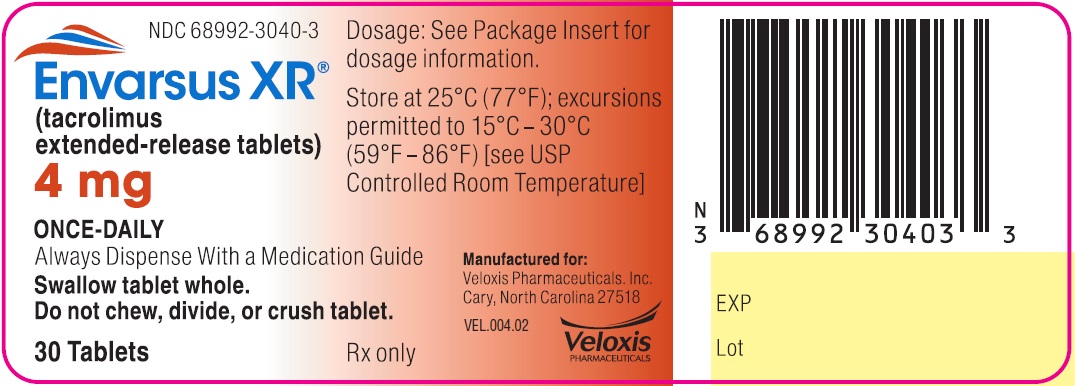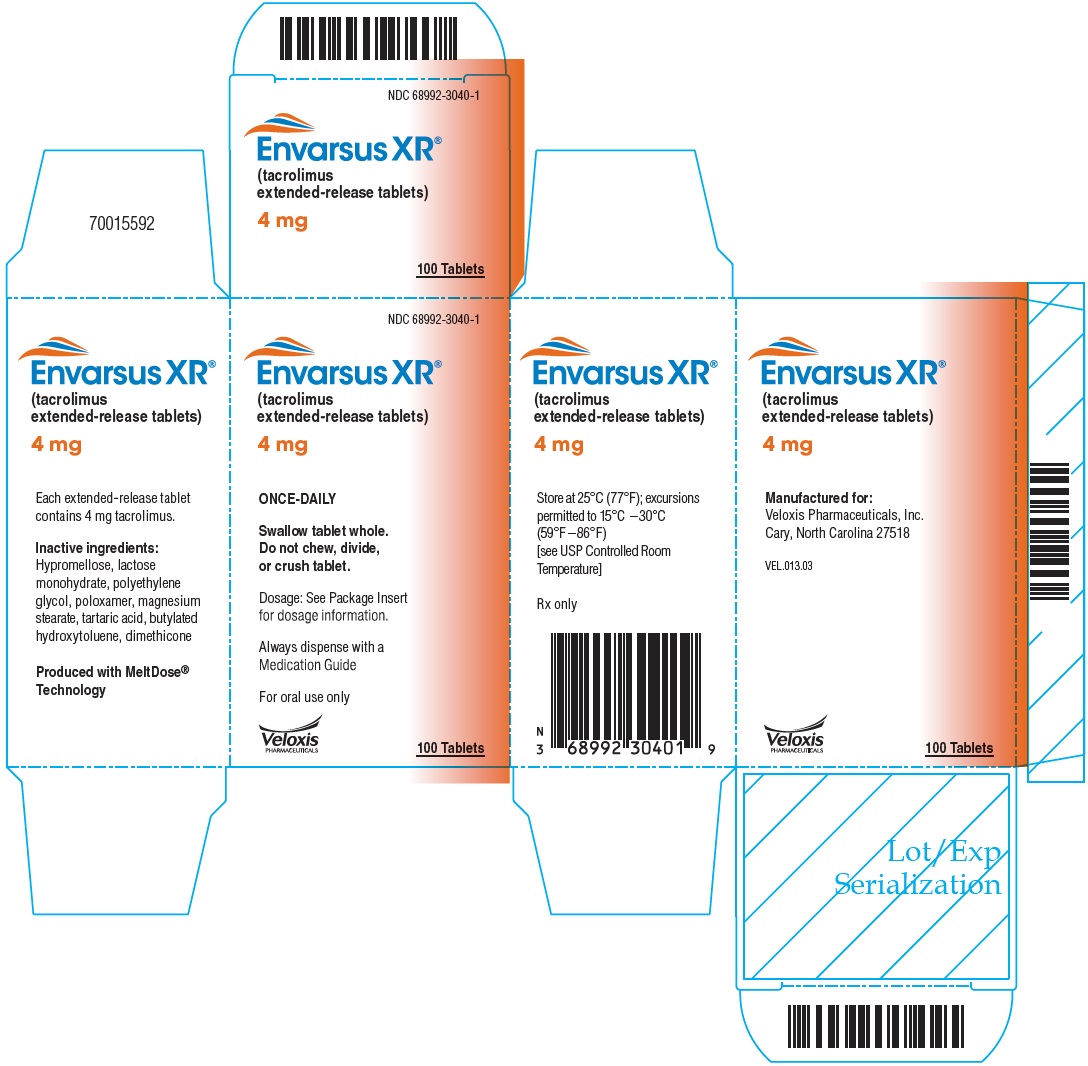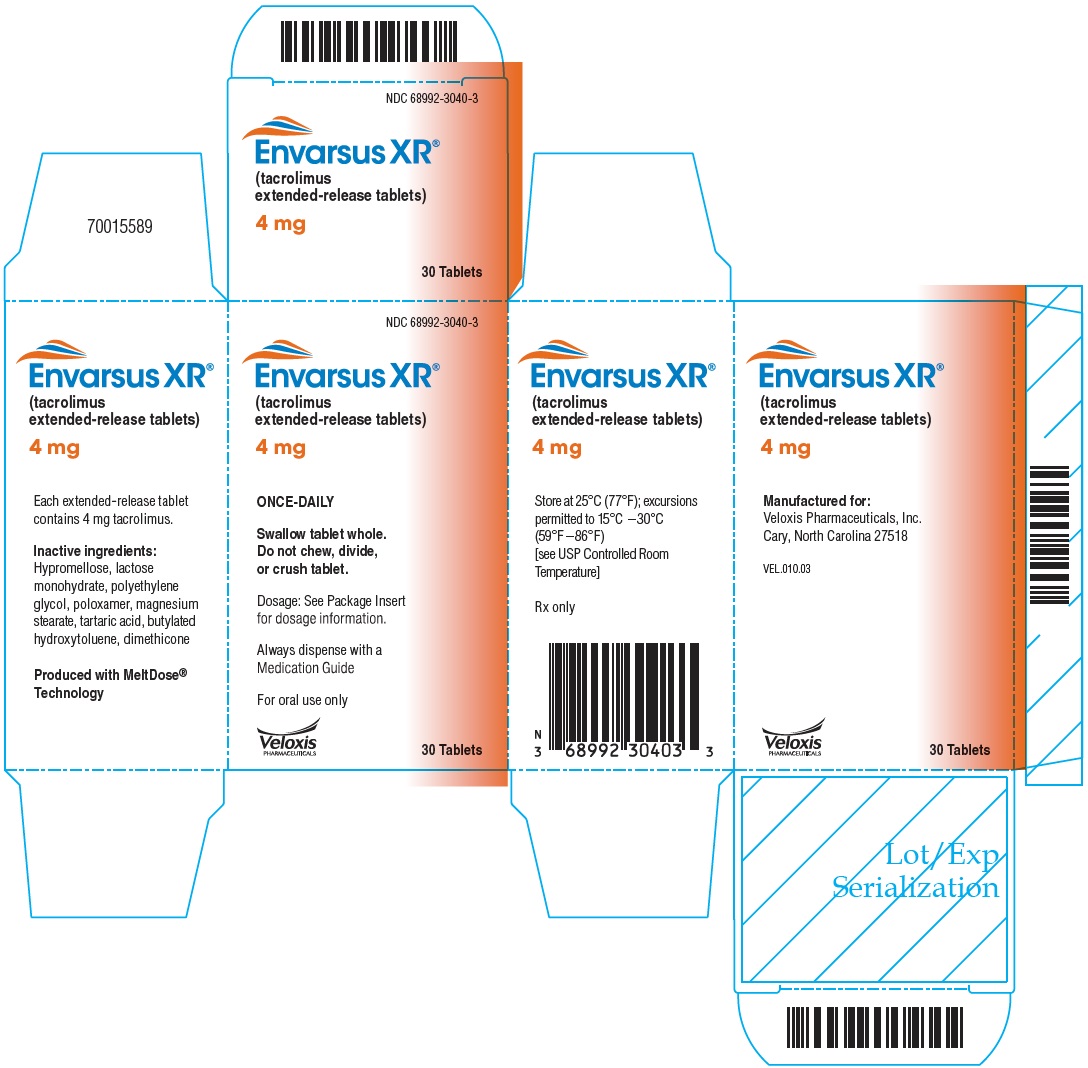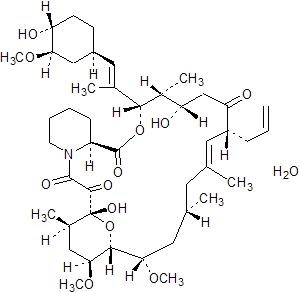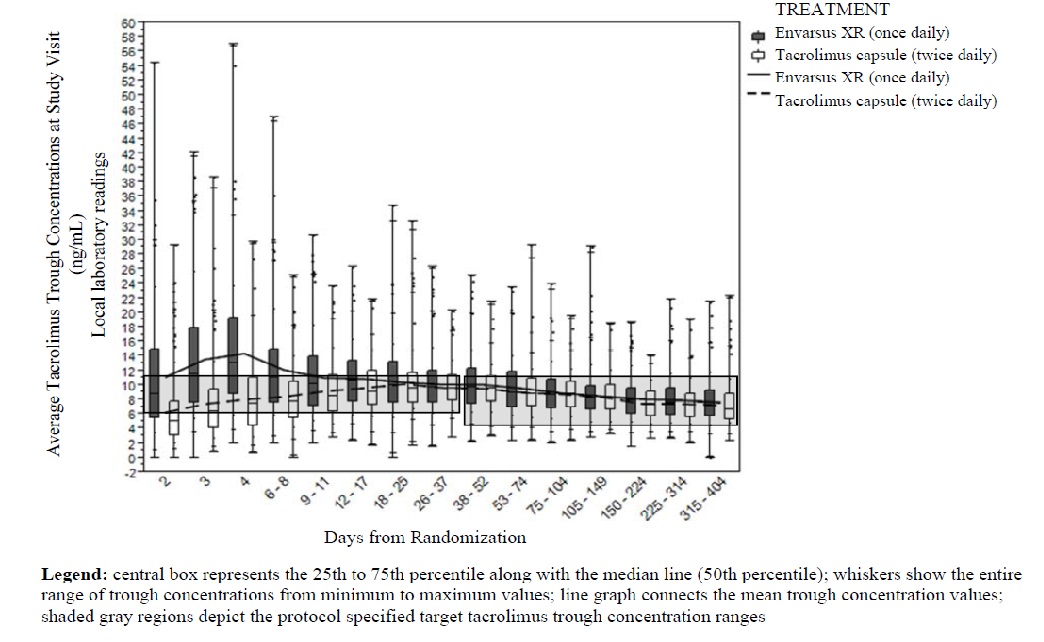 DRUG LABEL: Envarsus
NDC: 68992-3075 | Form: TABLET, EXTENDED RELEASE
Manufacturer: Veloxis Pharmaceuticals, Inc
Category: prescription | Type: HUMAN PRESCRIPTION DRUG LABEL
Date: 20250226

ACTIVE INGREDIENTS: TACROLIMUS 0.75 mg/1 1
INACTIVE INGREDIENTS: HYPROMELLOSES; LACTOSE MONOHYDRATE; POLYETHYLENE GLYCOL 6000; POLOXAMER 188; MAGNESIUM STEARATE; TARTARIC ACID; BUTYLATED HYDROXYTOLUENE; DIMETHICONE

HIGHLIGHTS OF PRESCRIBING INFORMATION

These highlights do not include all the information needed to use ENVARSUS XR® safely and effectively. See full prescribing information for ENVARSUS XR.
ENVARSUS XR® (tacrolimus extended-release tablets), for oral use
Initial U.S. Approval: 1994

WARNING: MALIGNANCIES AND SERIOUS INFECTIONS

See full prescribing information for complete boxed warning.

Increased risk for developing serious infections and malignancies with ENVARSUS XR or other immunosuppressants that may lead to hospitalization or death. (5.1, 5.2)

RECENT MAJOR CHANGES

Warnings and Precautions, Cannabidiol Drug Interactions (5.13) | 7/2023
Warnings and Precautions (5.5, 5.9, 5.10, 5.14) | 4/2024

1 INDICATIONS AND USAGE

ENVARSUS XR is a calcineurin-inhibitor immunosuppressant indicated for:

- The prophylaxis of organ rejection in de novo kidney transplant patients in combination with other immunosuppressants (1.1)
- The prophylaxis of organ rejection in kidney transplant patients converted from tacrolimus immediate-release formulations in combination with other immunosuppressants (1.2)

2 DOSAGE AND ADMINISTRATION

- Take once daily on empty stomach at the same time of the day, preferably in the morning. (2.1)
- Avoid eating grapefruit or drinking grapefruit juice or alcohol. (2.1)
- African-American patients may need to be titrated to higher dosages to achieve the target tacrolimus concentrations. (2.4)
- Patients with severe hepatic impairment may require a lower starting dose. (2.4)
- Frequent monitoring of trough concentrations is recommended. (2.5)

Recommended ENVARSUS XR Initial Dosage
 | Initial Oral Dosage | Whole Blood Trough Concentration Range
De novo kidney transplantation with antibody induction | 0.14 mg/kg/day | Month 1: 6-11 ng/mL >Month 1: 4-11 ng/mL
Conversion from tacrolimus immediate-release formulations | 80% of the pre-conversion dose of tacrolimus immediate-release | Titrate to 4-11 ng/mL

3 DOSAGE FORMS AND STRENGTHS

Extended-release tablets: 0.75 mg, 1 mg, 4 mg (3)

4 CONTRAINDICATIONS

Known hypersensitivity to tacrolimus or any of the ingredients (4)

5 WARNINGS AND PRECAUTIONS

- Not Interchangeable with Other Tacrolimus Products: Instruct patients or caregivers to recognize appearance of ENVARSUS XR tablets. (5.3)
- New Onset Diabetes after Transplant: Monitor blood glucose. (5.4)
- Nephrotoxicity (acute and/or chronic): May occur due to ENVARSUS XR, drug interactions or concomitant nephrotoxic drugs. Monitor renal function and tacrolimus blood concentrations; consider dosage reduction or temporary interruption of ENVARSUS. (5.5)
- Neurotoxicity: Including risk of posterior reversible encephalopathy syndrome (PRES); monitor for neurologic abnormalities; reduce dosage or discontinue ENVARSUS XR. (5.6)
- Hyperkalemia: Risk may be increased with other agents associated with hyperkalemia; monitor serum potassium levels. (5.7)
- Hypertension: May require antihypertensive therapy; monitor relevant drug interactions. (5.8)
- QT Prolongation: Consider obtaining electrocardiograms and monitoring electrolytes in patients at high risk. (5.10)
- Immunizations: Avoid live vaccines. (5.11)
- Pure Red Cell Aplasia: Consider discontinuation. (5.12)
- Thrombotic Microangiopathy, Including Hemolytic Uremic Syndrome and Thrombotic Thrombocytopenic Purpura: May occur, especially in patients with infections and certain concomitant medications. (5.14)

6 ADVERSE REACTIONS

- De novo kidney transplant patients: Most common adverse reactions (incidence ≥15%) include: diarrhea, anemia, urinary tract infection, hypertension, tremor, constipation, diabetes mellitus, peripheral edema, hyperkalemia and headache. (6.1)
- Conversion of kidney transplant patients from immediate-release to extended-release tacrolimus: Most common adverse reactions (incidence ≥10%) include: diarrhea and blood creatinine increased. (6.1)

To report SUSPECTED ADVERSE REACTIONS, contact Veloxis Pharmaceuticals, Inc. at 1-844-VELOXIS (1-844-835-6947) or FDA at 1-800-FDA-1088 or www.fda.gov/medwatch.

7 DRUG INTERACTIONS

- Risk of rejection with strong CYP3A inducers and risk of serious adverse reactions with strong CYP3A inhibitors: Adjust dose and monitor tacrolimus concentrations. (2.4, 5.9, 7.2)
- Therapeutic drug monitoring and dose reduction for ENVARSUS XR should be considered when ENVARSUS XR is co-administered with cannabidiol (2.5, 5.13, 7.3).
- See Full Prescribing Information for clinically significant drug interactions. (7.1, 7.2)

8 USE IN SPECIFIC POPULATIONS

Pregnancy: Can cause fetal harm. Advise pregnant women of the potential risk to the fetus. (8.1, 8.3)

FULL PRESCRIBING INFORMATION

WARNING: MALIGNANCIES AND SERIOUS INFECTIONS

Increased risk for developing serious infections and malignancies with ENVARSUS XR or other immunosuppressants that may lead to hospitalization or death [see Warnings and Precautions (5.1, 5.2)].

1 INDICATIONS AND USAGE

1.1 Prophylaxis of Organ Rejection in De Novo Kidney Transplant Patients

ENVARSUS XR is indicated for the prophylaxis of organ rejection in kidney transplant patients in combination with other immunosuppressants [see Clinical Studies (14.1)].

1.2 Prophylaxis of Organ Rejection in Stable Kidney Transplant Patients Converting from Immediate-Release Formulations

ENVARSUS XR is indicated for the prophylaxis of organ rejection in kidney transplant patients converted from tacrolimus immediate-release formulations, in combination with other immunosuppressants [see Clinical Studies (14.2)].

2 DOSAGE AND ADMINISTRATION

2.1 Important Administration Instructions

- ENVARSUS XR (tacrolimus extended-release tablets) is not interchangeable or substitutable with tacrolimus extended-release capsules, tacrolimus capsules, and tacrolimus for oral suspension. Under or overexposure to tacrolimus may result in graft rejection or other serious adverse reactions [see Warnings and Precautions (5.3)]. ENVARSUS XR should not be used without the supervision of a physician with experience in immunosuppressive therapy.
- ENVARSUS XR should be taken on an empty stomach consistently at the same time of the day, preferably in the morning to ensure consistent and maximum possible drug exposure, at least 1 hour before a meal or at least 2 hours after a meal [see Clinical Pharmacology (12.3)].
- Advise patients to swallow ENVARSUS XR tablets whole with fluid (preferably water); patients must not chew, divide, crush or dissovle the tablets.
- If a dose is missed, instruct the patient to take it as soon as possible within 15 hours after missing the dose. Beyond the 15-hour time frame, instruct the patient to wait until the usual scheduled time to take the next regular daily dose. Instruct the patient not to double the next dose.
- Patients should avoid eating grapefruit or drinking grapefruit juice or alcoholic beverage while taking ENVARSUS XR [see Drug Interactions (7.2)].

2.2 Dosing in De Novo Kidney Transplant Patients

The recommended starting dose of ENVARSUS XR in de novo kidney transplant patients is 0.14 mg/kg/day. Titrate ENVARSUS XR dosage based on clinical assessments of rejection and tolerability and to achieve whole blood trough concentration ranges (see Table 1).

Table 1. Recommended Tacrolimus Whole Blood Trough Concentration Ranges in Kidney Transplant Patients with Antibody Induction
Time Period Post Transplant | Target Tacrolimus Whole Blood Trough Concentration Ranges
During Month 1 | 6 to 11 ng/mL
> Month 1 | 4 to 11 ng/mL

2.3 Dosing for Conversion from Tacrolimus Immediate-Release Formulations

To convert from a tacrolimus immediate-release product to ENVARSUS XR, administer ENVARSUS XR once daily at a dose that is 80% of the total daily dose of the tacrolimus immediate-release product. Monitor tacrolimus whole blood trough concentrations and titrate ENVARSUS XR dosage to achieve whole blood trough concentration ranges of 4 to 11 ng/mL.

2.4 Dosing Adjustments in African-American Patients, Patients with Hepatic Impairment, Drug Interactions

African-American patients, compared to Caucasian patients, may need to be titrated to higher ENVARSUS XR dosages to attain comparable trough concentrations [see Use in Specific Populations (8.8), Clinical Pharmacology (12.3)].

Due to reduced clearance and prolonged half-life seen in patients with severe hepatic impairment (Child-Pugh ≥10) these patients may require a lower starting dosage of ENVARSUS XR [see Clinical Pharmacology (12.3)].

Dose adjustments of ENVARSUS XR may be necessary when administered concomitantly with CYP3A inducers or CYP3A inhibitors or cannabidiol [see Warnings and Precautions (5.9, 5.13), Drug Interactions (7.2, 7.3)].

2.5 Therapeutic Drug Monitoring

Measure tacrolimus whole blood trough concentrations at least two times on separate days during the first week after initiation of dosing and after any change in dosage, after a change in co-administration of CYP3A inducers and/or inhibitors or cannabidiol [see Drug Interactions (7)], or after a change in renal or hepatic function [see Use in Specific Populations (8.6, 8.7)]. When interpreting measured concentrations, consider that the time to achieve tacrolimus steady state is approximately 7 days after initiating or changing the ENVARSUS XR dose.

Monitor tacrolimus whole blood trough concentrations using a validated assay [e.g., immunoassays or high-performance liquid chromatography with tandem mass spectrometric detection (HPLC/MS/MS)]. The immunosuppressive activity of tacrolimus is mainly due to the parent drug rather than to its metabolites. Immunoassays may react with metabolites as well as the parent drug. Therefore, whole blood tacrolimus trough concentrations obtained with immunoassays may be numerically higher than concentrations obtained with an assay using HPLC/MS/MS. Comparison of the whole blood tacrolimus trough concentrations of patients to those described in the prescribing information and other published literature must be made with knowledge of the assay method(s) employed.

3 DOSAGE FORMS AND STRENGTHS

Oval, white to off-white uncoated extended-release tablets debossed with “TCS” on one side:

- 0.75 mg extended-release tablet: debossed with “0.75” on the other side.
- 1 mg extended-release tablet: debossed with “1” on the other side.
- 4 mg extended-release tablet: debossed with “4” on the other side.

4 CONTRAINDICATIONS

ENVARSUS XR is contraindicated in patients with known hypersensitivity to tacrolimus or to any of the ingredients in ENVARSUS XR.

5 WARNINGS AND PRECAUTIONS

5.1 Lymphoma and Other Malignancies

Immunosuppressants, including ENVARSUS XR, increase the risk of developing lymphomas and other malignancies, particularly of the skin. The risk appears to be related to the intensity and duration of immunosuppression rather than to the use of any specific agent. Examine patients for skin changes and advise to avoid or limit exposure to sunlight and UV light by wearing protective clothing and using a sunscreen with a high protection factor.

Post-transplant lymphoproliferative disorder (PTLD), associated with Epstein-Barr Virus (EBV), has been reported in immunosuppressed organ transplant patients. The risk of PTLD appears greatest in those individuals who are EBV seronegative. Monitor EBV serology during treatment.

5.2 Serious Infections

Immunosuppressants, including ENVARSUS XR, increase the risk of developing bacterial, viral, fungal, and protozoal infections, including opportunistic infections. These infections may lead to serious, including fatal, outcomes. Serious viral infections reported include:

- Polyomavirus-associated nephropathy (especially due to BK virus infection),
- JC virus-associated progressive multifocal leukoencephalopathy (PML), and
- Cytomegalovirus (CMV) infections: CMV seronegative transplant patients who receive an organ from a CMV seropositive donor are at highest risk of CMV viremia and CMV disease.

Monitor for the development of infection and adjust the immunosuppressive regimen to balance the risk of rejection with the risk of infection [see Adverse Reactions (6.1)].

5.3 Not Interchangeable with Other Tacrolimus Products-Medication Errors

Medication errors, including substitution and dispensing errors, between tacrolimus capsules and tacrolimus extended-release capsules were reported outside the U.S. This led to serious adverse reactions, including graft rejection, or other adverse reactions due to under- or over-exposure to tacrolimus. ENVARSUS XR is not interchangeable or substitutable with tacrolimus extended-release capsules, tacrolimus capsules or tacrolimus for oral suspension. Instruct patients and caregivers to recognize the appearance of ENVARSUS XR tablet [see Dosage Forms and Strengths (3)] and to confirm with their healthcare provider if a different product is dispensed or if dosing instructions have changed.

5.4 New Onset Diabetes after Transplant

ENVARSUS XR caused new onset diabetes after transplant (NODAT) in kidney transplant patients, which may be reversible in some patients. African-American and Hispanic kidney transplant patients are at an increased risk. Monitor blood glucose concentrations and treat appropriately [see Adverse Reactions (6.1) and Use in Specific Populations (8.8)].

5.5 Nephrotoxicity due to ENVARSUS XR and Drug Interactions

ENVARSUS XR, like other calcineurin-inhibitors, can cause acute or chronic nephrotoxicity in transplant patients due to its vasoconstrictive effect on renal vasculature, toxic tubulopathy and tubular-interstitial effects. Acute renal impairment associated with tacrolimus toxicity can result in high serum creatinine, hyperkalemia, decreased secretion of urea and hyperuricemia, and is usually reversible. In patients with elevated serum creatinine and tacrolimus whole blood trough concentrations greater than the recommended range, consider dosage reduction or temporary interruption of tacrolimus administration.

The risk for nephrotoxicity may increase when ENVARSUS XR is concomitantly administered with CYP3A inhibitors (by increasing tacrolimus whole blood concentrations) or drugs associated with nephrotoxicity (e.g., aminoglycosides, ganciclovir, amphotericin B, cisplatin, nucleotide reverse transcriptase inhibitors, protease inhibitors). When tacrolimus is used concurrently with CYP3A inhibitors or other known nephrotoxic drugs, monitor renal function and tacrolimus blood concentrations, and adjust dose of both tacrolimus and/or concomitant medications during concurrent use [see Adverse Reactions (6.1, 6.2) and Drug Interactions (7.2)].

5.6 Neurotoxicity

ENVARSUS XR may cause a spectrum of neurotoxicities. The most severe neurotoxicities include posterior reversible encephalopathy syndrome (PRES), delirium, seizure, and coma; others include tremors, paresthesias, headache, mental status changes, and changes in motor and sensory functions [see Adverse Reactions (6.1, 6.2)]. As symptoms may be associated with tacrolimus whole blood trough concentrations at or above the recommended range, monitor for neurologic symptoms and consider dosage reduction or discontinuation of ENVARSUS XR if neurotoxicity occurs.

5.7 Hyperkalemia

Mild to severe hyperkalemia, which may require treatment, has been reported with tacrolimus including ENVARSUS XR. Concomitant use of agents associated with hyperkalemia (e.g., potassium-sparing diuretics, ACE inhibitors, angiotensin receptor blockers) may increase the risk for hyperkalemia [see Adverse Reactions (6.1)]. Monitor serum potassium levels periodically during treatment.

5.8 Hypertension

Hypertension is a common adverse reaction of ENVARSUS XR therapy and may require antihypertensive therapy [see Adverse Reactions (6.1)]. Some antihypertensive drugs can increase the risk for hyperkalemia [see Warnings and Precautions (5.7)]. Calcium-channel blocking agents may increase tacrolimus blood concentrations and require dosage reduction of ENVARSUS XR [see Drug Interactions (7.2)].

5.9 Risk of Rejection with Strong CYP3A Inducers and Risk of Serious Adverse Reactions with Strong CYP3A Inhibitors

The concomitant use of strong CYP3A inducers may increase the metabolism of tacrolimus, leading to lower whole blood trough concentrations and greater risk of rejection. In contrast, the concomitant use of strong CYP3A inhibitors may decrease the metabolism of tacrolimus, leading to higher whole blood trough concentrations and greater risk of serious adverse reactions (e.g., neurotoxicity, QT prolongation) [see Warnings and Precautions (5.6, 5.10)]. Therefore, adjust ENVARSUS XR dose and monitor tacrolimus whole blood trough concentrations when co-administering ENVARSUS XR with strong CYP3A inhibitors (e.g., including but not limited to telaprevir, boceprevir, ritonavir, ketoconazole, itraconazole, voriconazole, clarithromycin) or strong CYP3A inducers (e.g., including but not limited to rifampin, rifabutin) [see Dosage and Administration (2.4, 2.5), Drug Interactions (7.2)]. A rapid, sharp rise in tacrolimus levels has been reported after co-administration with strong CYP3A4 inhibitors despite an initial reduction of tacrolimus dose. Early and frequent monitoring of tacrolimus whole blood trough levels is recommended [see Drug Interactions (7.2)].

5.10 QT Prolongation

ENVARSUS XR may prolong the QT/QTc interval and cause Torsades de pointes. Avoid ENVARSUS XR in patients with congenital long QT syndrome. Consider obtaining electrocardiograms and monitoring electrolytes (magnesium, potassium, calcium) periodically during treatment in patients with congestive heart failure, bradyarrhythmias, those taking certain antiarrhythmic medications or other products that lead to QT prolongation, and those with electrolyte disturbances (e.g., hypokalemia, hypocalcemia, or hypomagnesemia).

When co-administering ENVARSUS XR with other substrates and/or inhibitors of CYP3A, especially those that also have the potential to prolong the QT interval, a reduction in ENVARSUS XR dosage, monitoring of tacrolimus whole blood concentrations, and monitoring for QT prolongation is recommended [see Dosage and Administration (2.5), Drug Interactions (7.2)].

5.11 Immunizations

Whenever possible, administer the complete complement of vaccines before transplantation and treatment with ENVARSUS XR.

Avoid the use of live attenuated vaccines during treatment with ENVARSUS XR (e.g., intranasal influenza, measles, mumps, rubella, oral polio, BCG, yellow fever, varicella, and TY21a typhoid vaccines).

Inactivated vaccines noted to be safe for administration after transplantation may not be sufficiently immunogenic during treatment with ENVARSUS XR.

5.12 Pure Red Cell Aplasia

Cases of pure red cell aplasia (PRCA) have been reported in patients treated with tacrolimus. All of these patients reported risk factors for PRCA such as parvovirus B19 infection, underlying disease, or concomitant medications associated with PRCA. A mechanism for tacrolimus-induced PRCA has not been elucidated. If PRCA is diagnosed, consider discontinuation of ENVARSUS XR.

5.13 Cannabidiol Drug Interactions

When cannabidiol and ENVARSUS XR are co-administered, closely monitor for an increase in tacrolimus blood levels and for adverse reactions suggestive of tacrolimus toxicity. A dose reduction of ENVARSUS XR should be considered as needed when ENVARSUS XR is co-administered with cannabidiol [see Dosage and Administration (2.4, 2.5), Drug Interactions (7.3)].

5.14 Thrombotic Microangiopathy (TMA) Including Hemolytic Uremic Syndrome and Thrombotic Thrombocytopenic Purpura

Cases of thrombotic microangiopathy (TMA), including hemolytic uremic syndrome (HUS) and thrombotic thrombocytopenic purpura (TTP), have been reported in patients treated with ENVARSUS XR. TMA may have a multifactorial etiology. Risk factors for TMA that can occur in transplant patients include, for example, severe infections, graft-versus-host disease (GVHD), Human Leukocyte Antigen (HLA) mismatch, the use of calcineurin inhibitors and mammalian target of rapamycin (mTOR) inhibitors. These risk factors may, either alone or combined, contribute to the risk of TMA.

In patients with signs and symptoms of TMA, consider ENVARSUS XR as a risk factor. Concurrent use of ENVARSUS XR and mTOR inhibitors may contribute to the risk of TMA.

6 ADVERSE REACTIONS

The following clinically significant adverse drug reactions are discussed in greater detail in other sections of the labeling:

- Lymphoma and Other Malignancies [see Boxed Warning, Warnings and Precautions (5.1)]
- Serious Infections [see Boxed Warning, Warnings and Precautions (5.2)]
- New Onset Diabetes after Transplant [see Warnings and Precautions (5.4)]
- Nephrotoxicity due to ENVARSUS XR and Drug Interactions [see Warnings and Precautions (5.5)]
- Neurotoxicity [see Warnings and Precautions (5.6)]
- Hyperkalemia [see Warnings and Precautions (5.7)]
- Hypertension [see Warnings and Precautions (5.8)]
- QT Prolongation [see Warnings and Precautions (5.10)]
- Pure Red Cell Aplasia [see Warnings and Precautions (5.12)]
- Thrombotic Microangiopathy, Including Hemolytic Uremic Syndrome and Thrombotic Thrombocytopenic Purpura [see Warnings and Precautions (5.13)]

6.1 Clinical Studies Experience

Because clinical studies are conducted under widely varying conditions, adverse reaction rates observed in the clinical studies of a drug cannot be directly compared to rates in the clinical studies of another drug and may not reflect the rates observed in practice. In addition, the clinical studies were not designed to establish comparative differences across study arms with regards to the adverse reactions discussed below.

Study 1- Phase 3 Clinical Study in De Novo Kidney Transplant Recipients

Study 1 (NCT 01187953), was a Phase 3 randomized study in de novo kidney transplant patients that were treated with ENVARSUS XR (N=268) or tacrolimus [immediate-release] capsules (N=275) and concomitant immunosuppressants in a double-blind, randomized, multinational study [see Clinical Studies (14.1)]. The proportion of patients who discontinued treatment due to adverse reactions was 8.6% and 9.8% in the ENVARSUS XR and tacrolimus capsules treatment groups, respectively, through 12 months of treatment. The most common adverse reactions leading to discontinuation of study drug in the ENVARSUS XR treatment group were esophagitis, polyomavirus-associated nephropathy, graft dysfunction, complications of transplanted kidney, and diabetes mellitus, each resulting in 0.7% discontinuations among ENVARSUS XR treatment patients. In Study 1, de novo kidney transplant patients who received a starting dose of 0.17 mg/kg/day, which is higher than the recommended ENVARSUS XR starting dose of 0.14 mg/kg/day, exceeded the recommended target tacrolimus trough concentrations as high as 57 ng/mL during the first 1 to 2 weeks post-transplant [see Dosage and Administration (2.2)].

Infections

The overall incidence of infections, serious infections, and infections with identified etiology reported in de novo kidney transplant recipients treated with ENVARSUS XR or tacrolimus [immediate-release] capsules in Study 1 are shown in Table 2.

Table 2 Percentage of Patients with Infections Through 1 Year Post-Kidney Transplant in Study 1 a
 | ENVARSUS XR ± steroids, IL-2 receptor antagonist induction therapy, MMF/MPS or AZA N=268 | Tacrolimus [immediate-release] capsules ± steroids, IL-2 receptor antagonist induction therapy, MMF/MPS or AZA N=275
All infections | 70% | 65%
Urinary Tract Infections | 29% | 27%
Respiratory Infections | 28% | 24%
Bacterial Infections | 13% | 18%
Cytomegalovirus Infections | 11% | 9%
Fungal Infections | 9% | 8%
Gastrointestinal Infections | 6% | 4%
BK virus b | 6% | 9%
Serious Infections | 26% | 24%
MMF/MPS- Mycophenolate mofetil/mycophenolate sodium; AZA-azathioprine
a Study 1 was not designed to support comparative claims of ENVARSUS XR compared to tacrolimus [immediate-release] capsules for the adverse reactions reported in this table.
b BK virus-associated nephropathy (BKVAN) occurred in 1.5% (4/268) and 0.7% (2/275) in the ENVARSUS XR and tacrolimus capsules treatment groups, respectively.

New Onset Diabetes After Transplantation

New onset diabetes after transplantation (NODAT) was defined by the composite occurrence of fasting plasma glucose values ≥126 mg/dL, 2-hour post-prandial plasma glucose of at least 200 mg/dL (in oral glucose tolerance test) on two or more consecutive occasions post-baseline, insulin requirement for ≥31 days, an oral hypoglycemic agent use ≥31 days, or HbA1c ≥6.5% (at least 3 months after randomization) among kidney transplant patients with no medical history of diabetes. The incidence of NODAT for Study 1 through one year post-transplant is summarized in Table 3 below [see Warnings and Precautions (5.4)].

Table 3. Percentage of Patients with NODAT Through 1 Year Post-Kidney Transplant in Study 1 a
 | ENVARSUS XR ± steroids, IL-2 receptor antagonist induction therapy, MMF/MPS or AZA (N=88) | Tacrolimus [immediate-release] capsules ± steroids, IL-2 receptor antagonist induction therapy, MMF/MPS or AZA (N=74)
Composite NODAT b | 21% | 15%
HbA1c ≥6.5% | 13% | 8%
Fasting Plasma Glucose Values ≥126 mg/dL on 2 consecutive occurrences | 8% | 11%
Oral hypoglycemic use | 7% | 5%
Insulin use ≥31 days | 1% | 4%
MMF/MPS- Mycophenolate mofetil/mycophenolate sodium; AZA-azathioprine
a Study 1 was not designed to support comparative claims of ENVARSUS XR compared to tacrolimus [immediate-release] capsules for the adverse reactions reported in this table.
b Analyses restricted to patients at risk for NODAT.

Common Adverse Reactions

The incidence of adverse reactions that occurred in ≥10% of ENVARSUS XR-treated patients compared to tacrolimus [immediate-release] capsules through one year of treatment in Study 1 is shown by treatment group in Table 4 .

Table 4. Adverse Reactions (≥ 10%) in Kidney Transplant Patients Through 1 Year Post-Transplant in Study 1a
Adverse Reaction | ENVARSUS XR N=268 | Tacrolimus [immediate-release] capsules N=275
Diarrhea | 31% | 34%
Anemia | 26% | 29%
Urinary Tract Infection | 25% | 25%
Hypertension | 23% | 23%
Tremor | 19% | 17%
Constipation | 18% | 25%
Diabetes Mellitus | 16% | 14%
Peripheral Edema | 16% | 21%
Hyperkalemia | 15% | 11%
Headache | 15% | 10%
Hypophosphatemia | 13% | 15%
Leukopenia | 13% | 14%
Nausea | 13% | 15%
Insomnia | 13% | 11%
Increased Blood Creatinine | 12% | 14%
Hypomagnesemia | 12% | 12%
Hypokalemia | 12% | 12%
Hyperglycemia | 11% | 12%
a Study 1 was not designed to support comparative claims of ENVARSUS XR compared to tacrolimus [immediate-release] capsules for the adverse reactions reported in this table.

Study 2- Phase 2 Clinical Study in De Novo Kidney Transplant Recipients

Study 2 (NCT00765661) was an open-label Phase 2 study conducted in de novo kidney transplant patients randomized to once daily ENVARSUS XR (N=32) or twice daily tacrolimus [immediate-release] capsules (N=31). The study was conducted in the US and patients received an organ from a deceased or living donor. Pharmacokinetics were evaluated during the first 2 weeks with an additional 50-week treatment and follow-up to evaluate safety and efficacy [see Clinical Studies (14.1)].

The starting dosage was 0.14 mg/kg/day (given once daily) for ENVARSUS XR and 0.2 mg/kg/day (given twice daily) for tacrolimus [immediate-release] capsules. On Day 2 predose, the proportion of patients in the ENVARSUS XR group with tacrolimus trough concentration that were within, above, and below 6 to 11 ng/mL was 53%, 11%, and 37%, respectively. The starting dose of 0.14 mg/kg/day in Study 2 formed the basis of dosing recommendations in de novo kidney transplant patients.

There were no deaths or graft failures in Study 2. Two patients in each arm discontinued due to adverse events. The most common adverse reactions included infections and cardiovascular events, and were generally similar to those reported in Study 1.

Study 3- Phase 3 Clinical Studies in Stable Kidney Transplant Recipients Converted from Tacrolimus Capsules

In Study 3 (NCT00817206) stable kidney transplant patients were treated with ENVARSUS XR (N=162) or tacrolimus [immediate-release] capsules (N=162) and concomitant immunosuppressants in an open-label, randomized, multinational study [see Clinical Studies (14.2)]. The proportion of patients who discontinued treatment due to adverse reactions was 7.4% and 1.2% in the ENVARSUS XR and tacrolimus capsules treatment groups, respectively, through 12 months of treatment. The most common adverse reactions leading to discontinuation of study drug in the ENVARSUS XR treatment group was cardiac arrest (2 events).

Infections

The overall incidence of infections, serious infections, and infections with identified etiology reported in stable kidney transplant recipients treated with ENVARSUS XR or tacrolimus capsules are shown in Table 5.

Table 5. Percentage of Stable Patients with Infections Through 1 Year Post-Treatment in Study 3 a
 | ENVARSUS XR ± steroids, MMF/MPS or AZA N=162 | Tacrolimus [immediate-release] capsules± steroids, MMF/MPS or AZA N=162
All infections | 46% | 48%
Respiratory Infections | 26% | 28%
Urinary Tract Infections | 10% | 14%
Bacterial Infections | 7% | 5%
Fungal Infections | 4% | 4%
Gastrointestinal Infections | 4% | 5%
BK virus b | 2% | 2%
Cytomegalovirus Infections | 2% | 1%
Serious Infections | 8% | 9%
MMF/MPS- Mycophenolate mofetil/mycophenolate sodium; AZA-azathioprine
a The stable kidney transplant study was not designed to support comparative claims of ENVARSUS XR compared to tacrolimus capsules for the adverse reactions reported in this table.
b BK virus associated nephropathy (BKVAN) occurred in 1.2% (2/162) and 0.6% (1/162) in the ENVARSUS XR and tacrolimus capsules treatment groups, respectively.

New Onset Diabetes After Transplantation

New onset diabetes after transplantation (NODAT) was defined by the composite occurrence of fasting plasma glucose values ≥126 mg/dL, 2-hour postprandial plasma glucose of at least 200 mg/dL (in oral glucose tolerance test) on 2 or more consecutive occasions post-baseline, insulin requirement for ≥31 days, an oral hypoglycemic agent use ≥31 days, or HbA1c ≥6.5% (at least 3 months after randomization) among kidney transplant patients with no medical history of diabetes. The incidence of NODAT for the stable kidney transplant study through one year post-transplant is summarized in Table 6 below [see Warnings and Precautions (5.4)].

Table 6. Percentage of Stable Patients with NODAT Through 1 Year Post- Treatment in Study 3 a
 | ENVARSUS XR ± steroids, MMF/MPS or AZA (N=90) | Tacrolimus [immediate-release] capsules ± steroids, MMF/MPS or AZA (N=95)
Composite NODAT b | 10% | 11%
HbA1c ≥6.5% | 3% | 7%
Fasting Plasma Glucose Values ≥126 mg/dL on 2 consecutive occurrences | 8% | 6%
Oral hypoglycemic use | 1% | 1%
Insulin use ≥31 days | 1% | 0%
MMF/MPS- Mycophenolate mofetil/mycophenolate sodium; AZA-azathioprine
a The stable kidney transplant study was not designed to support comparative claims of ENVARSUS XR compared to tacrolimus capsules for the adverse reactions reported in this table.
b Analyses restricted to patients at risk for NODAT.

Common Adverse Reactions

In Study 3, the most common (≥10%) adverse reactions observed with Envarsus XR were diarrhea (14%), and blood creatinine increased (12%).

6.2 Postmarketing Experience

The following adverse reactions have been reported from marketing experience with tacrolimus in the U.S. and outside the U.S. Because these reactions are reported voluntarily from a population of uncertain size, it is not always possible to reliably estimate their frequency or establish a causal relationship to drug exposure. The following reactions have been included due to either their seriousness, frequency of reporting or strength of causal connection to ENVARSUS XR:

- Blood and Lymphatic System Disorders: Agranulocytosis, decreased blood fibrinogen, disseminated intravascular coagulation, hemolytic anemia, hemolytic uremic syndrome, leukopenia, febrile neutropenia, pancytopenia, prolonged activated partial thromboplastin time, pure red cell aplasia [see Warnings and Precautions (5.12)], thrombocytopenic purpura, thrombotic thrombocytopenic purpura, thrombotic microangiopathy
- Cardiac Disorders: Atrial fibrillation, atrial flutter, cardiac arrhythmia, cardiac arrest, electrocardiogram T wave abnormal, flushing, myocardial hypertrophy, myocardial infarction, myocardial ischaemia, pericardial effusion, QT prolongation, supraventricular extrasystoles, supraventricular tachycardia, Torsades de pointes, deep limb venous thrombosis, ventricular fibrillation
- Ear Disorders: Hearing loss including deafness
- Eye Disorders: Blindness, optic neuropathy, photophobia, optic atrophy
- Gastrointestinal Disorders: Abdominal pain, colitis, dysphagia, gastrointestinal perforation, impaired gastric emptying, intestinal obstruction, mouth ulceration, peritonitis, stomach ulcer
- Hepatobiliary Disorders: Bile duct stenosis, cholangitis, cirrhosis, fatty liver, hepatic cytolysis, hepatic failure, hepatic necrosis, hepatic steatosis, jaundice, hemorrhagic pancreatitis, necrotizing pancreatitis, venoocclusive liver disease, hepatitis (acute and chronic)
- Hypersensitivity Reactions: Hypersensitivity, Stevens-Johnson syndrome, toxic epidermal necrolysis, urticaria
- Immune System Disorders: Graft versus host disease (acute and chronic)
- Metabolism and Nutrition Disorders: Glycosuria, increased amylase, pancreatitis
- Musculoskeletal and Connective Tissue Disorders: Myalgia, polyarthritis, rhabdomyolysis
- Neoplasms: Lymphoma including EBV-associated lymphoproliferative disorder, PTLD [see Warnings and Precautions (5.1)]; leukemia
- Nervous System Disorders: Carpal tunnel syndrome, cerebral infarction, coma, dysarthria, flaccid paralysis, hemiparesis, mental disorder, mutism, nerve compression, posterior reversible encephalopathy syndrome (PRES) [see Warnings and Precautions (5.6)], progressive multifocal leukoencephalopathy (PML) sometimes fatal [see Warnings and Precautions (5.2)], quadriplegia, speech disorder, status epilepticus, syncope
- Renal and Urinary Disorder: Acute renal failure, hemorrhagic cystitis, hemolytic uremic syndrome, micturition disorder
- Respiratory, Thoracic and Mediastinal Disorders: Acute respiratory distress syndrome, interstitial lung disease, lung infiltration, pulmonary embolism, pulmonary hypertension, respiratory distress, respiratory failure
- Skin and Subcutaneous Tissue Disorders: Hyperpigmentation, photosensitivity, pruritus, rash

7 DRUG INTERACTIONS

7.1 Mycophenolic Acid

When ENVARSUS XR is prescribed with a given dose of mycophenolic acid (MPA) product, exposure to MPA is higher with ENVARSUS XR co-administration than with cyclosporine co-administration with MPA, because cyclosporine interrupts the enterohepatic recirculation of MPA while tacrolimus does not. Monitor for MPA associated adverse reactions and reduce the dose of concomitantly administered MPA products as needed.

7.2 Effects of Other Drugs/Substances on ENVARSUS XR

Table 7. Effects of Other Drugs/Substances on ENVARSUS XRa, d
Drug/Substance Class or Name | Drug Interaction Effect | Recommendations
Grapefruit or grapefruit juiceb | May increase tacrolimus whole blood trough concentrations and increase the risk of serious adverse reactions (e.g., neurotoxicity, QT prolongation) [see Warnings and Precautions (5.6, 5.9, 5.10)]. | Avoid grapefruit or grapefruit juice.
Alcohol | May modify the rate of tacrolimus release. | Avoid alcoholic beverages.
Strong CYP3A Inducersc, such as: Antimycobacterials (e.g., rifampin, rifabutin), anticonvulsants (e.g., phenytoin, carbamazepine and phenobarbital), St John’s Wort | May decrease tacrolimus whole blood trough concentrations and increase the risk of rejection [see Warnings and Precautions (5.9)]. | Increase ENVARSUS XR dose and monitor tacrolimus whole blood trough concentrations [see Dosage and Administration (2.5) and Clinical Pharmacology (12.3)].
Strong CYP3A Inhibitorsc,, such as: Protease inhibitors (e.g., nelfinavir, telaprevir, boceprevir, ritonavir or ritonavir containing products), azole antifungals (e.g., voriconazole, posaconazole, itraconazole, ketoconazole), antibiotics (e.g., clarithromycin, troleandomycin, chloramphenicol), nefazodone, Schisandra sphenanthera extracts, cobicistat | May increase tacrolimus whole blood trough concentrations and increase the risk of serious adverse reactions (e.g., neurotoxicity, QT prolongation). A rapid, sharp rise in tacrolimus levels may occur early, despite an immediate reduction of tacrolimus dose [see Warnings and Precautions (5.6, 5.9, 5.10)]. | Reduce ENVARSUS XR dose (for voriconazole and posaconazole, give one-third of the original dose) and adjust dose based on tacrolimus whole blood trough concentrations [see Dosage and Administration (2.5) and Clinical Pharmacology (12.3)]. Early and frequent monitoring of tacrolimus whole blood trough levels should start within 1-3 days and continue monitoring as necessary [see Warnings and Precautions (5.9)].
Mild or Moderate CYP3A Inhibitors, such as: antibiotics (e.g., erythromycin), calcium channel blockers (e.g., verapamil, diltiazem, nifedipine, nicardipine), amiodarone, danazol, ethinyl estradiol, cimetidine, lansoprazole and omeprazole, azole antifungals (e.g., clotrimazole, fluconazole, isavuconazole), imatinib, nilotinib, letermovir | May increase tacrolimus whole blood trough concentrations and increase the risk of serious adverse reactions (e.g., neurotoxicity, QT prolongation) [see Warnings and Precautions (5.6, 5.9, 5.10)]. | Monitor tacrolimus whole blood trough concentrations and reduce ENVARSUS XR dose if needed [see Dosage and Administration (2.5) and Clinical Pharmacology (12.3)].
Other drugs, such as: Magnesium and aluminum hydroxide antacids Metoclopramide | May increase tacrolimus whole blood trough concentrations and increase the risk of serious adverse reactions (e.g., neurotoxicity, QT prolongation) [see Warnings and Precautions (5.6 and 5.10)]. | Monitor tacrolimus whole blood trough concentrations and reduce ENVARSUS XR dose if needed [see Dosage and Administration (2.5) and Clinical Pharmacology (12.3)].
Mild or Moderate CYP3A Inducers, such as: Methylprednisolone, prednisone | May decrease tacrolimus whole blood trough concentrations. | Monitor tacrolimus whole blood trough concentrations and adjust ENVARSUS XR dose if needed [see Dosage and Administration (2.5)].
Caspofungin | May decrease tacrolimus whole blood trough concentrations. | Monitor tacrolimus whole blood trough concentrations and adjust ENVARSUS XR dose if needed [see Dosage and Administration (2.5)].
a ENVARSUS XR dosage adjustment recommendation based on observed effect of co-administered drug on tacrolimus exposures [see Clinical Pharmacology (12.3)], literature reports of altered tacrolimus exposures, or the other drug’s known CYP3A inhibitor/inducer status
b High dose or double strength grapefruit juice is a strong CYP3A inhibitor; low dose or single strength grapefruit juice is a moderate CYP3A inhibitor
c Strong CYP3A inhibitor/inducer, based on reported effect on exposures to immediate-release tacrolimus along with supporting in vitro CYP3A inhibitor/inducer data, or based on drug-drug interaction studies with midazolam (sensitive CYP3A probe substrate)
d A drug interaction study with voriconazole was conducted for ENVARSUS XR [see Clinical Pharmacology (12.3)]. No other drug-drug interaction studies were conducted with ENVARSUS XR.

Direct Acting Antiviral (DAA) Therapy

The pharmacokinetics of tacrolimus may be impacted by changes in liver function during DAA therapy, related to clearance of HCV virus. Close monitoring and potential dose adjustment of tacrolimus is warranted to ensure continued efficacy.

7.3 Cannabidiol

The blood levels of tacrolimus may increase upon concomitant use with cannabidiol. When cannabidiol and ENVARSUS XR are co-administered, closely monitor for an increase in tacrolimus blood levels and for adverse reactions suggestive of tacrolimus toxicity. A dose reduction of ENVARSUS XR should be considered as needed when ENVARSUS XR is co-administered with cannabidiol [see Dosage and Administration (2.5) and Warnings and Precautions (5.13)].

8 USE IN SPECIFIC POPULATIONS

8.1 Pregnancy

Pregnancy Exposure Registry

There is a pregnancy registry that monitors pregnancy outcomes in women exposed to ENVARSUS XR during pregnancy. The Transplantation Pregnancy Registry International (TPRI) is a voluntary pregnancy exposure registry that monitors outcomes of pregnancy in female transplant recipients and those fathered by male transplant recipients exposed to immunosuppressants including tacrolimus. Healthcare providers are encouraged to advise their patients to register by contacting the Transplantation Pregnancy Registry International at 1-877-955-6877 or https://www.transplantpregnancyregistry.org.

Risk Summary

Tacrolimus can cause fetal harm when administered to a pregnant woman. Data from postmarketing surveillance and TPRI suggest that infants exposed to tacrolimus in utero are at a risk of prematurity, birth defects/congenital anomalies, low birth weight, and fetal distress [see Human Data]. Advise pregnant women of the potential risk to the fetus.

Administration of oral tacrolimus to pregnant rabbits and rats throughout the period of organogenesis was associated with maternal toxicity/lethality, and an increased incidence of abortion, malformation and embryofetal death at clinically relevant doses (0.7 to 3.7 times the recommended clinical dose [0.14 mg/kg/day], on a mg/m² basis). Administration of oral tacrolimus to pregnant rats after organogenesis and throughout lactation produced maternal toxicity, effects on parturition, reduced pup viability and reduced pup weight at clinically relevant doses (1.2 to 3.7 times the recommended clinical dose, on a mg/m² basis). Administration of oral tacrolimus to rats prior to mating, and throughout gestation and lactation produced maternal toxicity/lethality, marked effects on parturition, embryofetal loss, malformations, and reduced pup viability at clinically relevant doses (1.2 to 3.7 times the recommended clinical dose, on a mg/m² basis). Interventricular septal defects, hydronephrosis, craniofacial malformations and skeletal effects were observed in offspring that died [see Animal Data].

The background risk of major birth defects and miscarriage in the indicated population is unknown. In the U.S. general population, the estimated background risk of major birth defects and miscarriage in clinically recognized pregnancies is 2 to 4 % and 15 to 20%, respectively.

Clinical Considerations

Disease-Associated Maternal and/or Embryo-Fetal Risk

Risks during pregnancy are increased in organ transplant recipients.

The risk of premature delivery following transplantation is increased. Pre-existing hypertension and diabetes confer additional risk to the pregnancy of an organ transplant recipient. Pre-gestational and gestational diabetes are associated with birth defects/congenital anomalies, hypertension, low birth weight and fetal death.

Cholestasis of pregnancy (COP) was reported in 7% of liver or liver-kidney (LK) transplant recipients, compared with approximately 1% of pregnancies in the general population. However, COP symptoms resolved postpartum and no long-term effects on the offspring were reported.

Maternal Adverse Reactions

ENVARSUS XR may increase hyperglycemia in pregnant women with diabetes (including gestational diabetes). Monitor maternal blood glucose levels regularly [see Warnings and Precautions (5.4)].

ENVARSUS XR may exacerbate hypertension in pregnant women and increase pre-eclampsia. Monitor and control blood pressure [see Warnings and Precautions (5.7, 5.8)].

Fetal/Neonatal Adverse Reactions

Renal dysfunction, transient neonatal hyperkalemia and low birth weight have been reported at the time of delivery in infants of mothers taking ENVARSUS XR.

Labor or Delivery

There is an increased risk for premature delivery (<37 weeks) following transplantation and maternal exposure to ENVARSUS XR.

Data

Human Data

There are no adequate and well controlled studies on the effects of tacrolimus in human pregnancy.

Safety data from the TPRI and postmarketing surveillance suggest infants exposed to tacrolimus in utero have an increased risk for miscarriage, pre-term delivery (<37 weeks), low birth weight (<2500 g), birth defects/congenital anomalies and fetal distress.

TPRI reported 450 and 241 total pregnancies in kidney and liver transplant recipients exposed to tacrolimus, respectively. The TPRI pregnancy outcomes are summarized in Table 8. In the table below, the number of recipients exposed to tacrolimus concomitantly with mycophenolic acid (MPA) products during the preconception and first trimester periods is high (27% and 29% for renal and liver transplant recipients, respectively). Because MPA products may also cause birth defects, the birth defect rate may be confounded and this should be taken into consideration when reviewing the data, particularly for birth defects. Birth defects observed include cardiac malformations, craniofacial malformations, renal/urogenital disorders, skeletal abnormalities, neurological abnormalities and multiple malformations.

Table 8. TPRI Reported Pregnancy Outcomes in Transplant Recipients with Exposure to Tacrolimus
 | Kidney | Liver
Pregnancy Outcomes* | 462 | 253
Miscarriage | 24.5% | 25%
Live births | 331 | 180
Pre-term delivery (< 37 weeks) | 49% | 42%
Low birth weight (< 2500 g) | 42% | 30%
Birth defects | 8%† | 5%

*Includes multiple births and terminations.
†Birth defect rate confounded by concomitant MPA products exposure in over half of offspring with birth defects.

Additional information reported by TPRI in pregnant transplant patients receiving tacrolimus included diabetes during pregnancy in 9% of kidney recipients and 13% of liver recipients and hypertension during pregnancy in 53% of kidney recipients and 16.2% of liver recipients.

Animal Data

Administration of oral tacrolimus to pregnant rabbits throughout organogenesis produced maternal toxicity and abortion at 0.32 mg/kg (0.7 times the recommended clinical dose based on body surface area). At 1 mg/kg (2.3 times the recommended clinical dose) embryofetal lethality and fetal malformations (ventricular hypoplasia, interventricular septal defect, bulbous aortic arch, stenosis of ductus arteriosus, omphalocele, gallbladder agenesis, skeletal anomalies) were observed. Administration of 3.2 mg/kg oral tacrolimus (3.7 times the recommended clinical dose) to pregnant rats throughout organogenesis produced maternal toxicity/lethality, embryofetal lethality and decreased fetal body weight in the offspring of C-sectioned dams; and decreased pup viability and interventricular septal defect in offspring of dams that delivered.

In a peri/postnatal development study, oral administration of tacrolimus to pregnant rats during late gestation (after organogenesis) and throughout lactation produced maternal toxicity, effects of parturition, and reduced pup viability at 3.2 mg/kg (3.7 times the recommended clinical dose); among these pups that died early, an increased incidence of kidney hydronephrosis was observed. Reduced pup weight was observed at 1mg/kg (1.2 times the recommended clinical dose).

Administration of oral tacrolimus to rats prior to mating, and throughout gestation and lactation produced maternal toxicity/lethality, embryofetal loss and reduced pup viability at 3.2 mg/kg (3.7 times the recommended clinical dose). Interventricular septal defects, hydronephrosis, craniofacial malformations and skeletal effects were observed in offspring that died. Effects on parturition (incomplete delivery of nonviable pups) were observed at 1 mg/kg (1.2 times the recommended clinical dose) [see Nonclinical Toxicology (13.1)].

8.2 Lactation

Risk Summary

Controlled lactation studies have not been conducted in humans; however tacrolimus has been reported to be present in human milk. The effects of tacrolimus on the breastfed infant, or on milk production have not been assessed. Tacrolimus is excreted in rat milk and in peri-/postnatal rat studies, exposure to tacrolimus during the postnatal period was associated with developmental toxicity in the offspring at clinically relevant doses [see Pregnancy (8.1), Nonclinical Toxicology (13.1)].

The development and health benefits of breastfeeding should be considered along with the mother’s clinical need for ENVARSUS XR and any potential adverse effects on the breastfed child from ENVARSUS XR or from the underlying maternal condition.

8.3 Females and Males of Reproductive Potential

Contraception

ENVARSUS XR can cause fetal harm when administered to pregnant women. Advise female and male patients of reproductive potential to speak with their healthcare provider on family planning options including appropriate contraception prior to starting treatment with ENVARSUS XR [see Use in Specific Populations (8.1), Nonclinical Toxicology (13.1)].

Infertility

Based on findings in animals, male and female fertility may be compromised by treatment with ENVARSUS XR [see Nonclinical Toxicology (13.1)].

8.4 Pediatric Use

The safety and effectiveness of ENVARSUS XR in pediatric patients have not been established.

8.5 Geriatric Use

Clinical studies of ENVARSUS XR did not include sufficient numbers of patients aged 65 and over to determine whether they respond differently from younger patients. In Studies 1, 2 and 3, there were 37 patients 65 years of age and older, and no patients were over 75 years [see Clinical Studies (14)]. Other reported clinical experience has not identified differences in responses between the elderly and younger patients. In general, dose selection for an elderly patient should be cautious, usually starting at the low end of the dosing range, reflecting the greater frequency of decreased hepatic, renal, or cardiac function, and of concomitant disease or other drug therapy.

8.6 Renal Impairment

The pharmacokinetics of tacrolimus in patients with renal impairment was similar to that in healthy subjects with normal renal function. However, due to its potential for nephrotoxicity, monitoring of renal function in patients with renal impairment is recommended; tacrolimus dosage should be reduced if indicated [see Warnings and Precautions (5.5) and Clinical Pharmacology (12.3)].

8.7 Hepatic Impairment

The mean clearance of tacrolimus was substantially lower in patients with severe hepatic impairment (mean Child-Pugh score: >10) compared to healthy subjects with normal hepatic function [see Clinical Pharmacology (12.3)]. With greater tacrolimus whole blood trough concentrations in patients with severe hepatic impairment, there is a greater risk of adverse reactions and dosage reduction is recommended [see Dosage and Administration (2.4)]. For patients with moderate hepatic impairment, monitor tacrolimus whole blood trough concentrations. For patients with mild hepatic impairment, no dosage adjustments are needed.

8.8 Race

African-American patients may need to be titrated to higher ENVARSUS XR dosages to attain comparable trough concentrations compared to Caucasian patients. The pharmacokinetics of ENVARSUS XR were evaluated in a study of 46 stable African-American kidney transplant recipients converted from tacrolimus immediate-release to ENVARSUS XR and indicated that an 80% conversion factor is appropriate for African-American patients [see Dosage and Administration (2.4), Clinical Pharmacology (12.3)].

African-American and Hispanic kidney transplant patients are at an increased risk for new onset diabetes after transplant. Monitor blood glucose concentrations and treat appropriately [see Warnings and Precautions (5.4)].

10 OVERDOSAGE

Postmarketing cases of overdose with tacrolimus have been reported. Overdosage adverse reactions included:

- nervous system disorders (tremor, headache, confusional state, balance disorders, encephalopathy, lethargy and somnolence)
- gastrointestinal disturbances (nausea, vomiting, and diarrhea)
- abnormal renal function (increased blood urea nitrogen and elevated serum creatinine)
- urticaria
- hypertension
- peripheral edema, and
- infections (one fatal postmarketing case of bilateral pneumopathy and CMV infection was attributed to tacrolimus extended-release capsules overdose).

Based on the poor aqueous solubility and extensive erythrocyte and plasma protein binding, it is anticipated that tacrolimus is not dialyzable to any significant extent; there is no experience with charcoal hemoperfusion. The oral use of activated charcoal has been reported in treating acute overdoses, but experience has not been sufficient to warrant recommending its use. General supportive measures and treatment of specific symptoms should be followed in all cases of overdosage.

11 DESCRIPTION

Tacrolimus is the active ingredient in ENVARSUS XR. Tacrolimus is a calcineurin-inhibitor immunosuppressant produced by Streptomyces tsukubaensis. Chemically, tacrolimus is designated as [3S-[3R*[E(1S*,3S*,4S*)],4S*,5R*,8S*,9E,12R*,14R*,15S*,16R*,18S*,19S*,26aR*]]-5,6,8,11,12,13,14,15,16,17,18,19,24,25,26,26a-hexadecahydro-5,19-dihydroxy-3-[2-(4-hydroxy-3-methoxycyclo-hexyl)-1-methylethenyl]-14,16-dimethoxy-4,10,12,18-tetramethyl-8-(2-propenyl)-15,19-epoxy-3H-pyrido[2,1-c][1,4]oxaazacyclotricosine-1,7,20,21(4H,23H)-tetrone, monohydrate.

The chemical structure of tacrolimus is:

Tacrolimus has an empirical formula of C44H69NO12•H2O and a formula weight of 822.03. Tacrolimus appears as white crystals or crystalline powder. It is practically insoluble in water, freely soluble in ethanol, and very soluble in methanol and chloroform.

ENVARSUS XR is available for oral administration as extended-release tablets containing the equivalent of 0.75 mg, 1 mg, or 4 mg of anhydrous tacrolimus USP. Inactive ingredients include hypromellose USP, lactose monohydrate NF, polyethylene glycol NF, poloxamer NF, magnesium stearate NF, tartaric acid NF, butylated hydroxytoluene NF, and dimethicone NF.

12 CLINICAL PHARMACOLOGY

12.1 Mechanism of Action

Tacrolimus binds to an intracellular protein, FKBP-12. A complex of tacrolimus-FKBP-12, calcium, calmodulin, and calcineurin (an ubiquitous mammalian intracellular enzyme) is then formed and the phosphatase activity of calcineurin inhibited. Such inhibition prevents the dephosphorylation and translocation of various factors such as the nuclear factor of activated T-cells (NF-AT) and nuclear factor kappa-light-chain-enhancer of activated B-cells (NF-κB).

Tacrolimus inhibits the expression and/or production of several cytokines that include interleukin (IL)-1 beta, IL-2, IL-3, IL-4, IL-5, IL-6, IL-8, IL-10, gamma interferon, tumor necrosis factor-alpha, and granulocyte macrophage colony stimulating factor. Tacrolimus also inhibits IL-2 receptor expression and nitric oxide release, induces apoptosis and production of transforming growth factor-beta that can lead to immunosuppressive activity. The net result is the inhibition of T-lymphocyte activation and proliferation as well as T-helper-cell-dependent B-cell response (i.e., immunosuppression).

12.3 Pharmacokinetics

Table 9 summarizes the pharmacokinetic (PK) parameters of tacrolimus following oral administration of once-daily ENVARSUS XR in healthy subjects and in kidney transplant patients, under fasted conditions. Whole blood tacrolimus concentrations in the pharmacokinetic studies were measured using validated HPLC/MS/MS assays.

Table 9. Pharmacokinetic Parameters of ENVARSUS XR by Study Day in Healthy Subjects and Kidney Transplant Patients Under Fasted Conditions
Population | ENVARSUS XR Dose | Dayb | Pharmacokinetic Parameters of ENVARSUS XR
Population | ENVARSUS XR Dose | Dayb | Cmaxc (ng/mL) | Tmaxd (hr) | AUC24c (ng•hr/mL) | C24h (ng/mL)
Healthy Subjectsa (n=19) | 2 mg 2 mg | Day 1 Day 10 | 11.9 ± 3.8 8.3 ± 2.9 | 14.0 [6 - 28] 8.0 [1.0-12.0] | 50 ± 14 140 ± 50 | 1.8 ± 0.6 4.6 ± 1.7
Adult Kidneya De novoe (n=21) | 11.8 mg f 10 mg 9.5 mg | Day 1 Day 7 Day 14 | 11.8 ± 7.2 25.1 ± 16.3 27.1 ± 13.4 | 8.0 [4-24] 6.0 [2-12] 4.0 [1-8] | 138 ± 80 335 ± 129 371 ± 104 | 5.2 ± 2.7 9.9 ± 4.4 11.4 ± 4.1j
Adult Kidneya De novo (n=10) | 15.5 mg g 11.4 mg 11.1 mg | Day 1 Day 14 Day 28 | 33.6 ± 21.8 31.1 ± 14.6 35.9± 18.7 | 6.0 [4-24] 4.0 [1-18] 4.0 [1-14] | 377 ± 257 376 ± 140 396 ± 150 | 11.0 ± 6.1 9.1 ± 3.0 10.5 ± 3.2
Adult Kidneya (≥ 6 months post- transplant) (n=47) | 5.3 mg | Day 7i | 13.5 ± 4.8 | 6.0 [1 - 16] | 216 ± 63 | 7.0 ± 2.3 j
Adult African- American Kidneyk (≥ 6 months post-transplant) (n=46) | 7.8 mg | Day 7i | 18.4 ± 7.2 | 5.0 [1 - 16] | 272 ± 97 | 7.8 ± 2.9 j
a) Healthy adult subjects (administered mg/day dose); Adult de novo kidney transplant patients (group average of administered mg/day dose); Adult kidney ≥ 6 months post-transplant (group average of administered mg/day dose of ENVARSUS XR, following conversion to 67% to 80% of the daily tacrolimus immediate -release capsules dose)
b) Day of ENVARSUS XR dosing and PK profiling
c) Arithmetic means ± S.D.
d) Median [range]
e) “De novo” refers to immunosuppression starting at the time of transplantation
f) Starting ENVARSUS XR dose = 0.14 mg/kg/day
g) Starting ENVARSUS XR dose = 0.17 mg/kg/day. De novo kidney transplant patients who received ENVARSUS XR starting dose of 0.17 mg/kg/day achieved higher than recommended target tacrolimus trough concentrations, as high as 57 ng/mL during the first 1 to 2 weeks post-transplant.
h) Tacrolimus trough concentration before the next dose
i) After 7 days of stable dosing with ENVARSUS XR
j) AUC0-24 –to- C24 correlation coefficient (r) at steady state was 0.80 or higher
k) Conversion to ENVARSUS XR at a mean dose of 80% of the total daily dose of tacrolimus immediate-release resulted in equivalent exposure with a 30% reduction in Cmax.

In de novo adult kidney transplant patients, the administration of ENVARSUS XR once daily at a starting dose of 0.14 mg/kg/day results in a tacrolimus systemic exposure (AUC24) on Day 1 post-transplant that is up to 10% lower than that of tacrolimus immediate-release capsules twice daily administered at a starting dose of 0.1 mg/kg/day, while similar tacrolimus trough concentrations (C24) are achieved. As steady state is achieved (typically within 7 days of stable ENVARSUS XR dosing), the AUC24 of ENVARSUS XR is approximately 15% higher than that of tacrolimus immediate-release capsules, at comparable trough concentrations (C24).

In adult kidney transplant patients ≥ 6 months post-transplant switched to ENVARSUS XR at 67% to 80% of the daily dose of tacrolimus immediate-release capsules, the steady state tacrolimus exposures (AUC24) and tacrolimus trough concentrations (C24) were comparable to the AUC24 and C24 measured prior to the switch. However, the mean Cmax estimate was 30% lower and the median Tmax was more prolonged (6 hours versus 2 hours) following administration of Envarsus XR as compared to that of tacrolimus immediate-release capsules.

Absorption

Absorption of tacrolimus from the gastrointestinal tract after oral administration is incomplete and variable. In de novo kidney transplant patients, the median time to achieve maximum blood concentrations (Cmax) of ENVARSUS XR was approximately 6 to 10 hours (Tmax) on day 1 post-transplant; the median Tmax at steady state was 4 to 6 hours. In healthy subjects, the oral bioavailability of ENVARSUS XR was approximately 50% higher as compared with both tacrolimus immediate-release and extended-release capsule formulations at steady state. In healthy subjects who received single ENVARSUS XR doses ranging from 5 mg to 10 mg, the mean AUC and C24 of tacrolimus increased linearly and the elimination half-life did not change with increasing doses.

Food Effects

The presence of a meal affects the absorption of tacrolimus; the rate and extent of absorption is greatest under fasted conditions. In 26 healthy subjects, administration of ENVARSUS XR following a high-fat breakfast reduced the systemic exposure (AUC) to tacrolimus by approximately 55% and the peak plasma concentration of tacrolimus (Cmax) by 22%, with no effect on the time to reach maximum plasma concentration (Tmax), compared to when ENVARSUS XR was administered under fasted conditions. ENVARSUS XR tablets should be taken preferably on an empty stomach at least 1 hour before a meal or at least 2 hours after a meal.

Chronopharmacokinetic Effect

In 26 healthy subjects, administration of ENVARSUS XR tablets in the evening resulted in a 15% lower AUC0-inf and a 20% lower C24, as compared to morning dosing.

Distribution

The plasma protein binding of tacrolimus is approximately 99% and is independent of concentration over a range of 5-50 ng/mL. Tacrolimus is bound mainly to albumin and alpha-1-acid glycoprotein, and has a high level of association with erythrocytes. The distribution of tacrolimus between whole blood and plasma depends on several factors, such as hematocrit, temperature at the time of plasma separation, drug concentration, and plasma protein concentration. In a U.S. trial in which tacrolimus was administered as immediate-release formulation, the ratio of whole blood concentration to plasma concentration averaged 35 (range 12 to 67).

Metabolism

The desired pharmacological activity of tacrolimus is primarily due to the parent drug. Tacrolimus is extensively metabolized by the mixed-function oxidase system, primarily the cytochrome P-450 system 3A (CYP3A4 and CYP3A5). A metabolic pathway leading to the formation of 8 possible metabolites has been proposed. Demethylation and hydroxylation were identified as the primary mechanisms of biotransformation in vitro. The major metabolite identified in incubations with human liver microsomes is 13-demethyl tacrolimus. In in vitro studies, a 31-demethyl metabolite has been reported to have the same activity as tacrolimus.

Excretion

In a mass balance study of orally administered radiolabeled tacrolimus to 6 healthy subjects, the mean recovery of the radiolabel was 94.9 ± 30.7%. Fecal elimination accounted for 92.6 ± 30.7% and urinary elimination accounted for 2.3 ± 1.1% of the total radiolabel administered. The elimination half-life based on radioactivity was 31.9 ± 10.5 hours, whereas it was 48.4 ± 12.3 hours based on tacrolimus concentrations. The mean clearance of radiolabel was 0.226 ± 0.116 L/hr/kg and the mean clearance of tacrolimus was 0.172 ± 0.088 L/hr/kg.

The elimination half-life of tacrolimus after oral administration of 2 mg ENVARSUS XR once-daily for 10 days was 31.0 ± 8.1 hours (mean ± SD) in 25 healthy subjects.

Specific Populations

Patients With Renal Impairment

Tacrolimus pharmacokinetics following a single administration of tacrolimus (administered as a continuous IV infusion) were determined in 12 patients (7 not on dialysis and 5 on dialysis, serum creatinine of 3.9±1.6 and 12.0±2.4 mg/dL, respectively) prior to their kidney transplant. The mean clearance of tacrolimus in patients with renal dysfunction given IV tacrolimus was similar to that in healthy subjects given tacrolimus IV and in healthy subjects given oral tacrolimus immediate-release [see Use In Specific Populations (8.6)].

Patients With Hepatic Impairment

Tacrolimus pharmacokinetics have been determined in 6 patients with mild hepatic impairment (mean Pugh score: 6.2) following single oral administration of tacrolimus immediate-release. The mean clearance of tacrolimus in patients with mild hepatic impairment was not substantially different from that in healthy subjects. Tacrolimus pharmacokinetics were studied in 6 patients with severe hepatic impairment (mean Pugh score: >10). The mean clearance was substantially lower in patients with severe hepatic impairment [see Dosage and Administration (2.3) and Use in Specific Populations (8.7)].

Racial or Ethnic Groups

The pharmacokinetics of ENVARSUS XR were evaluated in a study of 46 stable African American kidney transplant recipients converted from tacrolimus immediate-release to ENVARSUS XR. Approximately 80% of the African American patients were carriers of the active, wild type CYP3A5*1 allele. Regardless of genotype status, the PK results demonstrated similar exposure, lower Cmax, prolonged Tmax, and increased bioavailability compared to tacrolimus immediate-release [see Dosage and Administration (2.3) and Use in Specific Populations (8.8)].

Male and Female Patients

A formal trial to evaluate the effect of gender on tacrolimus pharmacokinetics has not been conducted. In a sub-group analysis from the two combined Phase 3 studies in kidney transplant recipients (Study 1 and Study 3) performed with ENVARSUS XR over one year of treatment, no gender-dependent differences in tacrolimus systemic exposures were observed.

Drug Interaction Studies

Because tacrolimus is metabolized mainly by CYP3A enzymes, drugs or substances known to inhibit these enzymes and/or are known CYP3A substrates may increase tacrolimus whole blood concentrations. Drugs known to induce CYP3A enzymes may decrease tacrolimus whole blood concentrations [see Warnings and Precautions (5.9) and Drug Interactions (7.2)].

Voriconazole: Co-administration of ENVARSUS XR with voriconazole following 400 mg BID of voriconazole resulted in a tacrolimus mean AUCinf increase by 2.62 fold and Cmax by 2.03 fold.

13 NONCLINICAL TOXICOLOGY

13.1 Carcinogenesis, Mutagenesis, Impairment of Fertility

Carcinogenesis

Carcinogenicity studies were conducted in male and female rats and mice. In the 80-week mouse oral study and in the 104-week rat oral study, no relationship of tumor incidence to tacrolimus dosage was found. The highest dose used in the mouse was 3mg/kg/day (0.84 times the AUC at the recommended clinical dose of 0.14 mg/kg/day) and in the rat was 5 mg/kg/day (0.24 times the AUC at the recommended clinical dose of 0.14 mg/kg/day) [see Boxed Warning and Warnings and Precautions (5.1)].

A 104-week dermal carcinogenicity study was performed in mice with tacrolimus ointment (0.03%-3%), equivalent to tacrolimus doses of 1.1-118 mg/kg/day or 3.3-354 mg/m^2/day. In the study, the incidence of skin tumors was minimal and the topical application of tacrolimus was not associated with skin tumor formation under ambient room lighting. However, a statistically significant elevation in the incidence of pleomorphic lymphoma in high-dose male (25/50) and female animals (27/50) and in the incidence of undifferentiated lymphoma in high-dose female animals (13/50) was noted in the mouse dermal carcinogenicity study. Lymphomas were noted in the mouse dermal carcinogenicity study at a daily dose of 3.5 mg/kg (0.1% tacrolimus ointment; 2.5-fold the human exposure in stable adult renal transplant patients converted from tacrolimus immediate-release product to ENVARSUS XR). No drug-related tumors were noted in the mouse dermal carcinogenicity study at a daily dose of 1.1 mg/kg (0.03% tacrolimus ointment). The relevance of topical administration of tacrolimus in the setting of systemic tacrolimus use is unknown.

The implications of these carcinogenicity studies are limited; doses of tacrolimus were administered that likely induced immunosuppression in these animals, impairing their immune system’s ability to inhibit unrelated carcinogenesis.

Mutagenesis

No evidence of genotoxicity was seen in bacterial (Salmonella and E. coli) or mammalian (Chinese hamster lung-derived cells) in vitro assays of mutagenicity, the in vitro CHO/HGPRT assay of mutagenicity, or in vivo clastogenicity assays performed in mice; tacrolimus did not cause unscheduled DNA synthesis in rodent hepatocytes.

Impairment of Fertility

Tacrolimus subcutaneously administered to male rats at paternally toxic doses of 2 mg/kg/day (2.3 times the recommended clinical dose based on body surface area) or 3 mg/kg/day (3.4 times the recommended clinical dose based on body surface area) resulted in a dose-related decrease in sperm count. Tacrolimus administered orally at 1mg/kg (1.2 times the recommended clinical dose based on body surface area) to male and female rats, prior to and during mating, as well as to dams during gestation and lactation, was associated with embryolethality and adverse effects on female reproduction. Effects on female reproductive function (parturition) and embryolethal effects were indicated by a higher rate of pre- and post-implantation loss and increased numbers of undelivered and nonviable pups. When administered at 3.2 mg/kg (3.7 times the recommended clinical dose based on body surface area), tacrolimus was associated with maternal and paternal toxicity as well as reproductive toxicity including marked adverse effects on estrus cycles, parturition, pup viability, and pup malformations.

14 CLINICAL STUDIES

14.1 Clinical Studies in De Novo Kidney Transplant Recipients

Study 1

Study 1 (NCT 01187953) was a Phase 3, 12-month, randomized, double-blind, multinational study comparing once daily ENVARSUS XR (N=268) to twice daily tacrolimus [immediate-release] capsules (N=275) in patients who received a de novo kidney transplant. Patients received the first dose of the study drug anytime within 48 hours of graft reperfusion. All patients received only IL-2 receptor antagonist induction therapy and concomitant treatment with mycophenolate mofetil (MMF) and corticosteroids. Approximately 97% of all patients received antibody induction therapy with basiliximab and 91% of all patients received corticosteroids and MMF.

The mean age of the study population was 46 years; 65% were male; 77% were Caucasian, 5% were African-American, 4% were Asian and 14% were categorized as other races. Living donors provided 49% of the organs and 51% of patients received a kidney transplant from a deceased donor. Patients with clinically relevant ECG abnormalities (including QTc prolongation and reversible ischemia) and clinically symptomatic congestive heart failure or patients with documented left ventricular ejection fraction of less than 45% were excluded. Patients with a panel reactive antibody (PRA) >30%, who received a kidney from a non-heart-beating donor or with cold ischemia time >30 hours were also excluded. Premature discontinuation from treatment at the end of one year occurred in 22% of ENVARSUS XR patients and 19% of tacrolimus [immediate-release] capsules patients.

Tacrolimus Therapy

In Study 1, de novo kidney transplant patients were dosed initially at a starting dosage of 0.17 mg/kg given once daily for ENVARSUS XR (approximately 1.2-fold higher than the recommended starting dosage) and 0.1 mg/kg/day (given twice daily) for tacrolimus [immediate-release] capsule, with doses then modified to maintain tacrolimus trough concentrations between 6-11 ng/mL for the first 30 days and then between 4-11 ng/L for the remainder of the study. In the first week of dosing, the tacrolimus doses administered were, on average, ~40% higher in the ENVARSUS XR group compared to the tacrolimus capsule group and were similar in both treatment groups from Day 10 to Week 3. Thereafter, tacrolimus doses were, on average, 10% to 20% lower for ENVARSUS XR than in the tacrolimus capsule group.

Tacrolimus whole blood trough concentrations were monitored on Days 2, 3, 4, 7, 10, 14, 21, 30, 45, 60, 90, 120, 180, 270, and 360. On Day 2 predose, the proportion of patients in the ENVARSUS XR group with tacrolimus trough concentration that were within, above and below the target tacrolimus trough concentration range of 6 to 11 ng/mL was 33%, 39%, and 28%, respectively, compared to 27%, 12%, and 61%, in the tacrolimus [immediate release] capsule group. The average tacrolimus trough concentrations (per local laboratory reading) for the ENVARSUS XR group were above the target range during the first week post-transplant, and higher than in the tacrolimus capsule group during the first 2 weeks post-transplant (see Figure 1). Thereafter, the mean tacrolimus trough concentrations were similar between the treatment groups.

Figure 1. Study 1 Tacrolimus Trough Concentrations by Treatment Group and Visits

Concomitant Immunosuppressive Drugs

In Study 1, the concomitant use of mycophenolate products was comparable between the ENVARSUS XR and tacrolimus [immediate-release] capsule treatment groups. Patients in both groups started MMF at an average dose of 1 gram twice daily. The MMF daily dose was reduced to less than 2 grams over the course of the study; the mean MMF equivalent total daily dose was approximately 1.5 grams at Month 12 in both treatment groups. Likewise, the average doses of corticosteroids were comparable between the two treatment groups throughout the 12-month study period. Majority (96% ENVARSUS XR and 99% tacrolimus [immediate-release] capsules) of the patients received two 20 mg doses of basiliximab for antibody induction.

Efficacy Results

The efficacy failure rates including patients who developed biopsy-proven acute rejection (BPAR), graft failure, death, and/or lost to follow-up at 12 months, as well as the rates of the individual events, are shown by treatment group in Table 10 for the intent-to-treat population.

Table 10. Incidence of BPAR, Graft Loss, Death or Lost to Follow-up at 12 Months in De Novo Kidney Transplant Patients in Study 1

 | ENVARSUS XR, MMF, steroids, and IL-2 receptor antagonist induction therapy N=268 | Tacrolimus [Immediate-Release] capsules, MMF, steroids, and IL-2 receptor antagonist induction therapy N=275
Overall Treatment Difference of efficacy failure compared to tacrolimus immediate-release (95% CI)a | -1.0% (-7.6%, 5.6%)
Treatment Failure | 50 (18.7%) | 54 (19.6%)
Biopsy Proven Acute Rejection | 36 (13.4%) | 37 (13.5%)
Graft Failure | 9 (3.4%) | 11 (4.0%)
Death | 8 (3.0%) | 8 (2.9%)
Lost to Follow-up | 4 (1.5%) | 5 (1.8%)
a 95% CI was calculated using normal approximation.

Glomerular Filtration Rates

Renal function was assessed as change from Day 30 (baseline) by eGFR calculated using the MDRD7 equation. Baseline eGFR values were 53.8 ml/min/1.73 m^2 and 54.4 ml/min/1.73 m^2, and 12 month eGFR values were 58.6 ml/min/1.73 m^2 and 59.8 ml/min/1.73 m^2 in the ENVARSUS XR and the tacrolimus [immediate-release] capsule groups, respectively, maintaining the small difference of approximately 1ml/min/1.73 m^2 between the treatment groups.

Study 2

Study 2 (NCT 00765661) was an open-label Phase 2 study conducted in de novo kidney transplant patients randomized to once daily ENVARSUS XR (N=32) or twice daily tacrolimus [immediate-release] capsule(N=31). The study was conducted in the US and patients received an organ from a deceased or living donor. Pharmacokinetics were evaluated during the first 2 weeks with an additional 50-week treatment and follow-up to evaluate safety and efficacy.

Study 2 did not have any exclusion criteria based on cardiac disease or ECG findings but patients who received a kidney from a non-heart-beating donor or with cold ischemia time ≥ 36 hours were excluded. Patients were randomized within 12 hours after transplantation and received the first dose of the study drug within 48 hours of graft reperfusion. Induction treatment and concomitant immunosuppressive therapy were allowed per center-specific practices.

The mean age of study population was 47 years (range 23-69); 68% were male; 75% were Caucasian, 21% were African- American, 5% were Asian. Two patients in each group withdrew early from the study due to adverse events.

Tacrolimus Therapy

In Study 2, de novo kidney transplant patients received a starting dosage of 0.14 mg/kg/day (given once daily) for ENVARSUS XR and 0.20 mg/kg/day (given twice daily) for tacrolimus [immediate-release] capsule. On Day 2 predose, the proportion of patients in the ENVARSUS XR group with tacrolimus trough concentration that were within, above, and below 6 to 11 ng/mL was 53%, 11%, and 37%, respectively. In Study 1, the proportion of de novo kidney transplant patients receiving a starting dose of 0.1 mg/kg/day of tacrolimus capsules that were within, above, and below 6 to 11 ng/mL on Day 2 predose was 27%, 12%, and 61%, respectively.

Concomitant Immunosuppressive Drugs

In Study 2, concomitant therapy with mycophenolate products or azathioprine, corticosteroids, and antibody induction was permitted but not required. The mean daily MMF, prednisone, and antibody induction doses were similar between the ENVARSUS XR and tacrolimus capsules treatment groups.

Efficacy

There were no deaths or graft failures in Study 2. Acute rejection rates at 12 months were 3.1% (1/32) in the ENVARSUS XR group and 6.5% (2/31) in the tacrolimus capsules group and 2 patients (one in each group) were lost to follow-up.

14.2 Conversion Study from Tacrolimus Capsules in Stable Kidney Transplant Recipients

Study 3

The conversion study, Study 3 (NCT00817206), was a Phase 3 randomized, open-label, multinational study evaluating once daily ENVARSUS XR when used to replace tacrolimus [immediate-release] capsules administered twice daily for maintenance immunosuppression to prevent acute allograft rejection in stable adult kidney transplant patients. Patients who received a kidney transplant 3 months to 5 years before study entry and on a stable dose of tacrolimus [immediate-release] capsules of at least 2 mg per day and tacrolimus whole blood trough concentrations between 4 and 15 ng/mL were randomized to 1) switch from twice daily tacrolimus capsules to once daily ENVARSUS XR (N=163) or 2) continue tacrolimus capsules twice daily (N=163). MMF or mycophenolate sodium (MPS), or azathioprine (AZA) and/or corticosteroids were allowed as concomitant immunosuppressants during the study period according to the standard of care at the participating site.

The mean age of study population was 50 years; 67% were male; 73% were Caucasian, 22% were African-American, 2% were Asian and 3% were categorized as other races. Living donors provided 35% of the organs and 65% of patients received a kidney transplant from a deceased donor. Premature discontinuation from treatment at the end of one year occurred in 13% of ENVARSUS XR patients and 6% of tacrolimus capsule patients.

Tacrolimus Therapy

In Study 3, stable kidney transplant patients converted to ENVARSUS XR at an average daily dose that was 80% of their tacrolimus [immediate-release] capsules daily dose prior to conversion. Mean tacrolimus whole blood trough concentrations were maintained within a relatively narrow range throughout the duration of the study for both the ENVARSUS XR conversion group and the tacrolimus capsules continuation group. At Week 1 (after 7 days of stable dosing), the mean ± SD tacrolimus trough concentrations were 7.2 ± 3.1 ng/mL for the ENVARSUS XR conversion group and 7.7 ± 2.5 for the tacrolimus capsules continuation group; the baseline values were 7.8 ± 2.3, and 8.0 ± 2.3, respectively.

MMF Therapy

In Study 3, the average daily mycophenolate equivalent doses were comparable between the ENVARSUS XR and tacrolimus capsules treatment groups.

Efficacy Results

The efficacy failure rates including patients who developed BPAR, graft failure, death, and/or lost to follow-up at 12 months, as well as the rates of the individual events, are shown by treatment group in Table 11 for the modified intent-to-treat population.

Table 11. Incidence of BPAR, Graft Loss, Death or Lost to Follow-up at 12 Months in Stable Kidney Transplant Patients in Study 3
 | ENVARSUS XR ± Steroids ± MMF, MPS, or AZA N=162 | Tacrolimus [Immediate-Release] Capsules ± Steroids ± MMF, MPS, or AZA N=162
Treatment Failure | 4 (2.5%) | 4 (2.5%)
Overall Treatment Difference of efficacy failure compared to tacrolimus immediate-release (95% CI)a | 0% (-4.2%, 4.2%)
Biopsy Proven Acute Rejection | 2 (1.2%) | 2 (1.2%)
Graft Failure | 0% | 0%
Death | 2 (1.2%) | 1 (0.6%)
Lost to Follow-up | 0% | 1 (0.6%)
a 95% CI was calculated using an exact method that is based on the standardized statistic and inverting a 2-sided test

Glomerular Filtration Rates

The mean estimated glomerular filtration rates (eGFR), using the Modification of Diet in Renal Disease 7 (MDRD7) formula, were 61.5 ml/min/1.73 m^2 and 60.0 ml/min/1.73 m^2 at baseline (Day 0) and 62.0 ml/min/1.73 m^2 and 61.4 ml/min/1.73 m^2 at 12 months in the ENVARSUS XR and tacrolimus capsules treatment groups, respectively.

16 HOW SUPPLIED/STORAGE AND HANDLING

ENVARSUS XR is supplied in round HDPE bottles with twist-off caps (see Table 12); the statement ‘ONCE-DAILY’ appears on its labels.

Table 12. Strengths of ENVARSUS XR
Strength | Description | NDC
0.75 mg | Oval, white to off-white uncoated extended-release tablet, debossed with “0.75” on one side and “TCS” on the other side. | 30-count (NDC 68992-3075-3) 100-count (NDC 68992-3075-1)
1 mg | Oval, white to off-white uncoated extended-release tablet, debossed with “1” on one side and “TCS” on the other side. | 30-count (NDC 68992-3010-3) 100-count (NDC 68992-3010-1)
4 mg | Oval, white to off-white uncoated extended-release tablet, debossed with “4” on one side and “TCS” on the other side. | 30-count (NDC 68992-3040-3) 100-count (NDC 68992-3040-1)

Store and Dispense
Store at 25 °C (77 °F); excursions permitted to 15 °C to 30 °C (59 °F to 86 °F) [see USP Controlled Room Temperature].

17 PATIENT COUNSELING INFORMATION

Advise the patient to read the FDA-approved patient labeling (Medication Guide).

17.1 Administration

Advise patients to:

- Inspect their ENVARSUS XR medicine when they receive a new prescription and before taking it. If the appearance of the tablet is not the same as usual, or if dosage instructions have changed, advise patients to contact their healthcare provider as soon as possible to make sure that you have the right medicine. Other tacrolimus products cannot be substituted for ENVARSUS XR [see Warnings and Precautions (5.3)].
- Take once-daily ENVARSUS XR at the same time every day (preferably in the morning) on an empty stomach. at least 1 hour before or at least 2 hours after a meal to ensure consistent and maximum possible drug concentrations in the blood.
- Swallow tablet whole with liquid, preferably water. Do not chew, divide or crush tablet.
- Avoid alcoholic beverages, grapefruit, and grapefruit juice while on ENVARSUS XR [see Dosage and Administration (2.1) and Drug Interactions (7.2)].
- Take a missed dose as soon as possible but not more than 15 hours after the scheduled time (i.e., for a missed 8 AM dose, take it no later than 10 PM). Beyond the 15-hour timeframe, instruct the patient to wait until the usual scheduled time the following morning to take the next regularly scheduled dose. Do not take two doses at the same time [see Dosage and Administration (2.1)].

17.2 Development of Lymphoma and Other Malignancies

Inform patients that they are at an increased risk of developing lymphomas and other malignancies, particularly of the skin, due to immunosuppression. Advise patients to limit exposure to sunlight and ultraviolet (UV) light by wearing protective clothing and use a sunscreen with a high protection factor [see Boxed Warning and Warnings and Precautions (5.1)].

17.3 Increased Risk of Infection

Inform patients that they are at an increased risk of developing a variety of infections, including opportunistic infections, due to immunosuppression and to contact their physician if they develop any symptoms of infection such as fever, sweats or chills, cough or flu-like symptoms, muscle aches, or warm, red, painful areas on the skin [see Boxed Warning and Warnings and Precautions (5.2)].

17.4 New Onset Diabetes After Transplant

Inform patients that ENVARSUS XR can cause diabetes mellitus and should be advised to contact their physician if they develop frequent urination, increased thirst or hunger [see Warnings and Precautions (5.4)].

17.5 Nephrotoxicity

Inform patients that ENVARSUS XR can have toxic effects on the kidney that should be monitored. Advise patients to attend all visits and complete all blood tests ordered by their medical team [see Warnings and Precautions (5.5)].

17.6 Neurotoxicity

Inform patients that they are at risk of developing adverse neurologic effects including seizure, altered mental status, and tremor. Advise patients to contact their physician should they develop vision changes, delirium, or tremors [see Warnings and Precautions (5.6)].

17.7 Hyperkalemia

Inform patients that ENVARSUS XR can cause hyperkalemia. Monitoring of potassium levels may be necessary, especially with concomitant use of other drugs known to cause hyperkalemia [see Warnings and Precautions (5.7)].

17.8 Hypertension

Inform patients that ENVARSUS XR can cause high blood pressure which may require treatment with anti-hypertensive therapy. Advise patients to monitor their blood pressure [see Warnings and Precautions (5.8)].

17.9 Thrombotic Microangiopathy

Inform patients that ENVARSUS XR can cause blood clotting problems. The risk of this occurring increases when patients take ENVARSUS XR and sirolimus or everolimus concomitantly, or when patients develop certain infections. Advise them to seek medical attention promptly if they develop fever, petequiae or bruises, fatigue, confusion, jaundice, oliguria [see Warnings and Precautions (5.13)].

17.10 Drug Interactions

Instruct patients to tell their healthcare providers when they start or stop taking any concomitant medications, including prescription and non-prescription medicines, natural or herbal remedies, dietary supplements and vitamins. Some medications could alter tacrolimus concentrations in the blood and thus may require the adjustment of the dosage of ENVARSUS XR. Advise patients to avoid grapefruit, grapefruit juice and alcoholic beverages [see Warnings and Precautions (5.9, 5.13) and Drug Interactions (7)].

17.11 Pregnancy, Lactation and Infertility

Inform women of childbearing potential that ENVARSUS XR can harm the fetus. Instruct male and female patients to discuss with their healthcare provider family planning options including appropriate contraception. Also discuss with pregnant patients the risks and benefits of breastfeeding their infant [see Use in Specific Populations (8.1, 8.2, 8.3)].

Encourage female transplant patients who become pregnant and male patients who have fathered a pregnancy, exposed to immunosuppressants including tacrolimus, to enroll in the voluntary Transplantation Pregnancy Registry International. To enroll or register, patients can call the toll-free number 1-877-955-6877 or https://www.transplantpregnancyregistry.org.

Based on animal studies, ENVARSUS XR may affect fertility in males and females [see Nonclinical Toxicology (13.1)].

17.12 Immunizations

Inform patients that ENVARSUS XR can interfere with the usual response to immunizations and that they should avoid live vaccines [see Warnings and Precautions (5.11)].

Product of Germany

Manufactured by:
Rottendorf Pharma GmbH
59320 Ennigerloh
North Rhine-Westphalia
Germany

Manufactured for:
Veloxis Pharmaceuticals, Inc.
Cary, North Carolina 27518
United States

MEDICATION GUIDE
ENVARSUS XR® (En var' sus XR)
(tacrolimus extended-release tablets)
for oral use

Read this Medication Guide before you start taking ENVARSUS XR and each time you get a refill. There may be new information. This information does not take the place of talking with your healthcare provider about your medical condition or your treatment. If you have any questions about ENVARSUS XR, ask your healthcare provider or pharmacist.

What is the most important information I should know about ENVARSUS XR?
ENVARSUS XR can cause serious side effects, including:

1. Increased risk of cancer. People who take ENVARSUS XR have an increased risk of getting some kinds of cancer, including skin and lymph gland cancer (lymphoma).
2. Increased risk of infection. ENVARSUS XR is a medicine that affects your immune system. ENVARSUS XR can lower the ability of your immune system to fight infections. Serious infections can happen in people receiving ENVARSUS XR that can cause death.
  Call your healthcare provider right away if you have symptoms of an infection such as:

- fever
- sweats or chills

- cough or flu-like symptoms
- muscle aches

- warm, red, or painful areas on your skin

What is ENVARSUS XR?

- ENVARSUS XR is a prescription medicine used with other medicines to help prevent organ rejection in people who have had a kidney transplant.
- ENVARSUS XR is an extended-release tablet and is not the same as tacrolimus extended-release capsules, tacrolimus immediate-release capsules or tacrolimus for oral suspension. Your healthcare provider should decide what medicine is right for you.

It is not known if Envarsus XR is safe and effective in children.

Who should not take ENVARSUS XR?

Do not take ENVARSUS XR if you:

- are allergic to tacrolimus or any of the ingredients in ENVARSUS XR. See the end of this Medication Guide for a complete list of ingredients in ENVARSUS XR.

What should I tell my doctor before taking ENVARSUS XR?

Before you take ENVARSUS XR, tell your healthcare provider about all your medication conditions, including if you:

- plan to receive any live vaccines. Ask your healthcare provider if you are not sure if your vaccine is a live vaccine.
- have or have had liver, kidney or heart problems.
- are pregnant or plan to become pregnant. ENVARSUS XR may harm your unborn baby.
  - If you are able to become pregnant, you should use effective birth control before and during treatment with ENVARSUS XR. Talk to your healthcare provider about birth control methods that may be right for you.
  - Males who have female partners that are able to become pregnant should also use effective birth control before and during treatment with ENVARSUS XR. Talk to your healthcare provider before starting treatment with ENVARSUS XR about birth control methods that may be right for you.
  - There is a pregnancy registry for females who become pregnant and males who have fathered a pregnancy during treatment with ENVARSUS XR. The purpose of this registry is to collect information about your health and of your baby. To enroll in this voluntary registry, call 1-877- 955-6877 or register at https://www.transplantpregnancyregistry.org.
- are breastfeeding or plan to breastfeed. ENVARSUS XR passes into your breast milk. You and your healthcare provider should decide if you will breastfeed while taking ENVARSUS XR

Tell your healthcare provider about all the medicines you take, including prescription and over-the-counter medicines, vitamins, natural, herbal or nutritional supplements.

ENVARSUS XR may affect the way other medicines work, and other medicines may affect how ENVARSUS XR works.

Especially tell your healthcare provider if you take:

- sirolimus (RAPAMUNE):
- everolimus
- cyclosporine (GENGRAF, NEORAL, and SANDIMMUNE)
- medicines called aminoglycosides that are used to treat bacterial infections
- ganciclovir (CYTOVENE IV, VALCYTE)
- amphotericin B (ABELCET, AMBISOME)
- cisplatin
- antiviral medicines called nucleoside reverse transcriptase inhibitors
- antiviral medicines called protease inhibitors
- water pill (diuretic)
- medicine to treat high blood pressure
- erythromycin
- danazol
- ethyinyl estradiol
- cimetidine
- lansoprazole
- omeprazole
- azole antifungals
- imatinib
- nilotinib
- nelfinavir (VIRACEPT)
- telaprevir (INCIVEK)
- boceprevir)
- ritonavir (PAXLOVID, KALETRA, NORVIR, TECHNIVIE, VIEKIRA PAK, VIEKIRA XR)
- letermovir (PREVYMIS)
- ketoconazole
- itraconazole (ONMEL, SPORANOX)
- voriconazole (VFEND)
- posaconazole
- caspofungin (CANCIDAS)
- clarithromycin (BIAXIN, BIAXIN XL, PREVPAC)
- troleandomycin
- chloramphenicol
- nefazodone
- Schisandra sphenanthera extracts
- cobicistat
- rifampin (RIFADIN, RIFAMATE, RIFATER, RIMACTANE)
- rifabutin (MYCOBUTIN)
- medicine to treat seizures (phenytoin, carbamazepine, phenobarbital
- St. John’s Wort
- amiodarone (NEXTERONE, PACERONE)
- cannabidiol (EPIDIOLEX)
- magnesium and aluminum hydroxide antacids
- metoclopramide
- methylprednisolone
- prednisone

Ask your healthcare provider or pharmacist if you are not sure if you take any of the medicines listed above. ENVARSUS XR may affect the way other medicines work, and other medicines may affect how ENVARSUS XR works.

Know the medicines you take. Keep a list of your medicines and show it to your healthcare provider and pharmacist when you get a new medicine.

How should I take ENVARSUS XR?

- Take ENVARSUS XR exactly as your healthcare provider tells you to take it.
- Your healthcare provider may change your dose of ENVARSUS XR if needed. Do not stop taking or change your dose of ENVARSUS XR without talking to your healthcare provider.
- Take ENVARSUS XR 1-time daily with fluid (preferably water) on an empty stomach, at least 1 hour before or at least 2 hours after a meal, at the same time each day (preferably in the morning). Taking ENVARSUS XR at the same time each day helps to keep the amount of ENVARSUS XR in your body at a steady level.
- Take ENVARSUS XR tablets whole. Do not chew, divide, crush, or dissolve ENVARSUS XR tablets before swallowing. If you cannot swallow ENVARSUS XR tablets whole, tell your healthcare provider.
- If you miss your dose of ENVARSUS XR, it should be taken as soon as possible, but no longer than 15 hours after missing your dose. If the time after missing your dose is more than 15 hours, the missed dose should be skipped and the next dose should be taken the following morning at your regularly scheduled time. Do not take 2 doses at the same time.
- If you take too much ENVARSUS XR, call your healthcare provider or go to the nearest hospital emergency room right away.

What should I avoid while taking ENVARSUS XR?

- Live vaccines such as the flu vaccine through your nose, measles, mumps, rubella, polio by mouth, BCG (TB vaccine), yellow fever, chicken pox (varicella), or typhoid.
- Exposure to sunlight and UV light such as tanning machines. Wear protective clothing and use a sunscreen.
- You should not eat grapefruit or drink grapefruit juice while taking ENVARSUS XR.
- You should not drink alcohol while taking ENVARSUS XR.

What are the possible side effects of ENVARSUS XR?

ENVARSUS XR may cause serious side effects, including:

- See “What the most important information I should know about ENVARSUS XR?”
- problems from medication errors such as graft rejection and other serious reactions. People who take ENVARSUS XR have sometimes been given the wrong medicine because some medicines have the same ingredient (tacrolimus) as ENVARSUS XR. Check your ENVARSUS XR when you get a new prescription to make sure you have received the right medicine.
  - Call your healthcare provider right away if you think you were given the wrong medicine.
  - Ask your healthcare provider or pharmacist if you are not sure what ENVARSUS XR should look like.
- high blood sugar (diabetes). High blood sugar is a serious, but common side effect of ENVARSUS XR. Your healthcare provider may do certain tests to check for diabetes while you take ENVARSUS XR. Call your healthcare provider right away if you have:

- frequent urination
- confusion
- fruity smell on your breath

- increased thirst or hunger
- drowsiness
- nausea, vomiting, or stomach pain

- blurred vision
- loss of appetite

- kidney problems. Kidney problems are serious, but common side effects of ENVARSUS XR. Your healthcare provider may do certain tests to check for kidney function while you take ENVARSUS XR.
- nervous system problems. Nervous system problems are a serious, but common side effect of ENVARSUS XR. Call your healthcare provider right away if you get any of these symptoms while taking ENVARSUS XR:
- high levels of potassium in your blood. High levels of potassium in your blood are a serious, but common side effect of ENVARSUS XR. Your healthcare provider may do certain tests to check your potassium level while you take ENVARSUS XR.

- confusion
- numbness and tingling
- vision changes

- coma
- headache
- muscle tremors

- seizures

- high blood pressure. High blood pressure is a serious, but common side effect of ENVARSUS XR. Your healthcare provider will monitor your blood pressure while you take ENVARSUS XR.
- changes in the electrical activity of your heart (QT prolongation). Your healthcare provider may do certain tests to check your heart function while you take ENVARSUS XR.
- severe low blood cell count (anemia). Your healthcare provider may stop your treatment with ENVARSUS XR if you develop a severe low blood cell count.
- blood clotting problems: Tell your healthcare provider right away if you have fever and bruising under the skin that may appear as red dots, with or without unexplained tiredness, confusion, yellowing of the skin or eyes, decreased urination. When taken with sirolimus or everolimus, or when you develop certain infections, the risk of developing these symptoms may increase.

The most common side effects of ENVARSUS XR in people who received a kidney transplant are:

- diarrhea
- low red blood cell count (anemia)

- urinary tract infection
- constipation

- swelling in the arms, hands, or legs (peripheral edema)

The most common side effects of ENVARSUS XR in people who are switching from immediate-release tacrolimus to ENVARSUS XR are diarrhea and high blood creatinine.

These are not all the possible side effects of ENVARSUS XR. For more information, ask your healthcare provider or pharmacist.
Call your doctor for medical advice about side effects. You may report side effects to FDA at 1-800-FDA-1088.

How should I store ENVARSUS XR?

- Store ENVARSUS XR at room temperature between 68 ºF to 77 ºF (20 °C to 25 ºC).
- Safely throw away medicine that is out of date or no longer needed.

Keep ENVARSUS XR and all medicines out of reach of children.

General information about the safe and effective use of ENVARSUS XR.

Medicines are sometimes prescribed for purposes other than those listed in a Medication Guide. Do not use ENVARSUS XR for a condition for which it was not prescribed. Do not give ENVARSUS XR to other people, even if they have the same symptoms that you have. It may harm them.

This Medication Guide summarizes the most important information about ENVARSUS XR. If you would like more information, talk with your healthcare provider. You can ask your pharmacist or healthcare provider for information about ENVARSUS XR that is written for health professionals.

What are the ingredients in ENVARSUS XR?

Active ingredient: tacrolimus USP.
Inactive ingredients: hypromellose USP, lactose monohydrate NF, polyethylene glycol NF, poloxamer NF, magnesium stearate NF, tartaric acid NF, butylated hydroxytoluene NF, and dimethicone NF.

Manufactured by: Rottendorf Pharma GmbH, 59320 Ennigerloh, North Rhine-Westphalia, Germany
Manufactured for: Veloxis Pharmaceuticals, Inc., Cary, North Carolina 27518, United States
For more information, go to www.ENVARSUSXR.com or call 1-844-Veloxis (1-844-835-6947).

This Medication Guide has been approved by the U.S. Food and Drug Administration.

Revised: 4/2024

PACKAGE LABEL

PRINCIPAL DISPLAY PANEL - Envarsus 0.75 mg 30 Count Carton Label

NDC 68992-3075-3

Envarsus XR®

(tacrolimus
extended-release tablets)

0.75 mg

ONCE-DAILY

Swallow tablet whole.

Do not chew, divide,
or crush tablet.

Dosage: See Package Insert
for dosage information.

Always dispense with a
Medication Guide

For oral use only

Veloxis PHARMACEUTICALS

30 Tablets

PRINCIPAL DISPLAY PANEL - Envarsus 0.75 mg 30 Count Bottle Label

NDC 68992-3075-3

Envarsus XR®

(tacrolimus
extended-release tablets)

0.75 mg

ONCE-DAILY

Always Dispense With a Medication Guide

Swallow tablet whole.

Do not chew, divide, or crush tablet.

30 Tablets Rx only

Veloxis PHARMACEUTICALS

PRINCIPAL DISPLAY PANEL - Envarsus 0.75 mg 100 Count Carton Label

NDC 68992-3075-1

Envarsus XR®

(tacrolimus
extended-release tablets)

0.75 mg

ONCE-DAILY

Swallow tablet whole.

Do not chew, divide,
or crush tablet.

Dosage: See Package Insert
for dosage information.

Always dispense with a
Medication Guide

For oral use only

Veloxis PHARMACEUTICALS

100 Tablets

PRINCIPAL DISPLAY PANEL - Envarsus 0.75 mg 100 Count Bottle Label

NDC 68992-3075-1

Envarsus XR®

(tacrolimus
extended-release tablets)

0.75 mg

ONCE-DAILY

Always Dispense With a Medication Guide

Swallow tablet whole.

Do not chew, divide, or crush tablet.

100 Tablets Rx only

Veloxis PHARMACEUTICALS

PRINCIPAL DISPLAY PANEL - Envarsus 1 mg 30 Count Carton Label

NDC 68992-3010-3

Envarsus XR®

(tacrolimus
extended-release tablets)

1 mg

ONCE-DAILY

Swallow tablet whole.

Do not chew, divide,
or crush tablet.

Dosage: See Package Insert
for dosage information.

Always dispense with a
Medication Guide

For oral use only

Veloxis PHARMACEUTICALS

30 Tablets

PRINCIPAL DISPLAY PANEL - Envarsus 1 mg 30 Count Bottle Label

NDC 68992-3010-3

Envarsus XR®

(tacrolimus
extended-release tablets)

1 mg

ONCE-DAILY

Always Dispense With a Medication Guide

Swallow tablet whole.

Do not chew, divide, or crush tablet.

30 Tablets Rx only

Veloxis PHARMACEUTICALS

PRINCIPAL DISPLAY PANEL - Envarsus 1 mg 100 Count Carton Label

NDC 68992-3010-1

Envarsus XR®

(tacrolimus
extended-release tablets)

1 mg

ONCE-DAILY

Swallow tablet whole.

Do not chew, divide,
or crush tablet.

Dosage: See Package Insert
for dosage information.

Always dispense with a
Medication Guide

For oral use only

Veloxis PHARMACEUTICALS

100 Tablets

PRINCIPAL DISPLAY PANEL - Envarsus 1 mg 100 Count Bottle Label

NDC 68992-3010-1

Envarsus XR®

(tacrolimus
extended-release tablets)

1 mg

ONCE-DAILY

Always Dispense With a Medication Guide

Swallow tablet whole.

Do not chew, divide, or crush tablet.

100 Tablets Rx only

Veloxis PHARMACEUTICALS

PRINCIPAL DISPLAY PANEL - Envarsus 4 mg 30 Count Carton Label

NDC 68992-3040-3

Envarsus XR®

(tacrolimus
extended-release tablets)

4 mg

ONCE-DAILY

Swallow tablet whole.

Do not chew, divide,
or crush tablet.

Dosage: See Package Insert
for dosage information.

Always dispense with a
Medication Guide

For oral use only

Veloxis PHARMACEUTICALS

30 Tablets

PRINCIPAL DISPLAY PANEL - Envarsus 4 mg 30 Count Bottle Label

NDC 68992-3040-3

Envarsus XR®

(tacrolimus
extended-release tablets)

4 mg

ONCE-DAILY

Always Dispense With a Medication Guide

Swallow tablet whole.

Do not chew, divide, or crush tablet.

30 Tablets Rx only

Veloxis PHARMACEUTICALS

PRINCIPAL DISPLAY PANEL - Envarsus 4 mg 100 Count Carton Label

NDC 68992-3040-1

Envarsus XR®

(tacrolimus
extended-release tablets)

4 mg

ONCE-DAILY

Swallow tablet whole.

Do not chew, divide,
or crush tablet.

Dosage: See Package Insert
for dosage information.

Always dispense with a
Medication Guide

For oral use only

Veloxis PHARMACEUTICALS

100 Tablets

PRINCIPAL DISPLAY PANEL - Envarsus 4 mg 100 Count Bottle Label

NDC 68992-3040-1

Envarsus XR®

(tacrolimus
extended-release tablets)

4 mg

ONCE-DAILY

Always Dispense With a Medication Guide

Swallow tablet whole.

Do not chew, divide, or crush tablet.

100 Tablets

Veloxis PHARMACEUTICALS